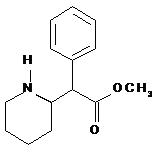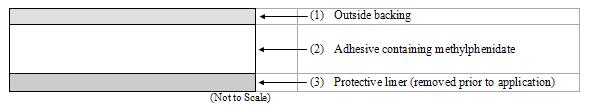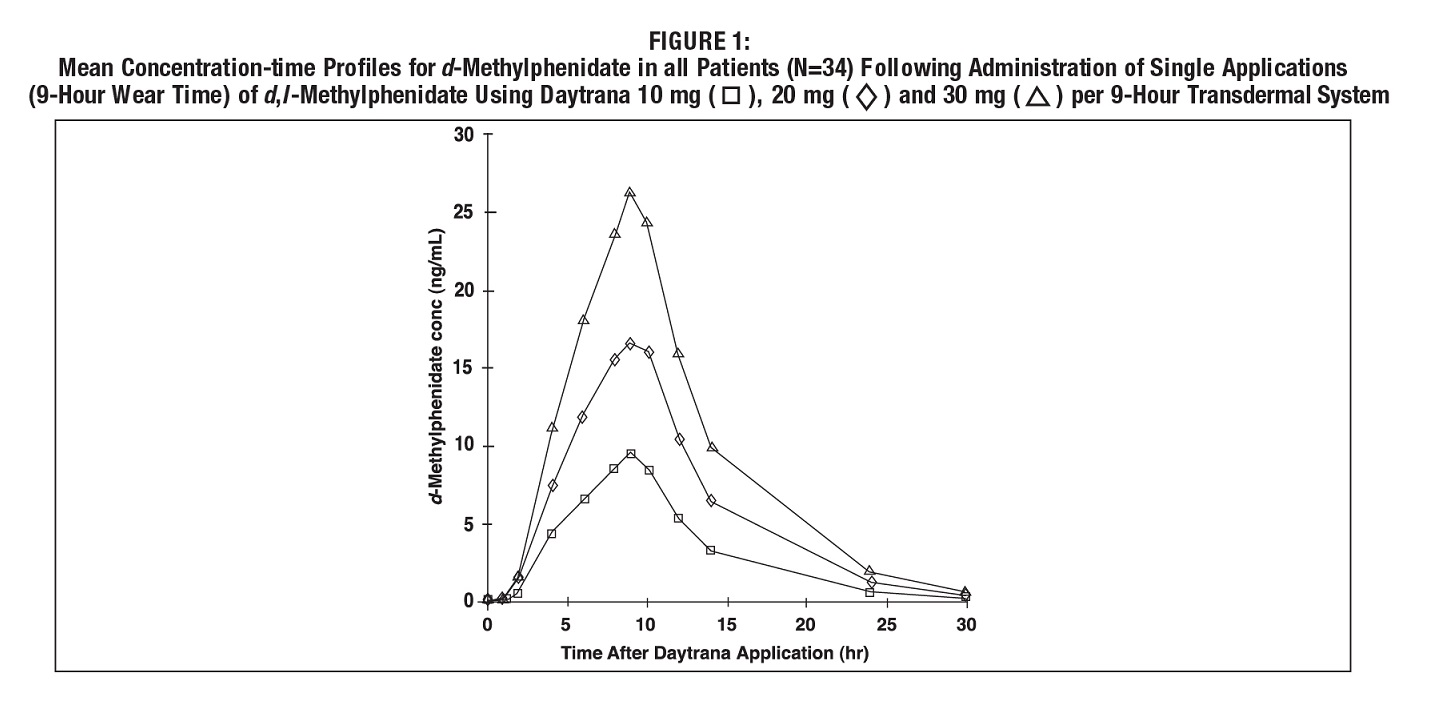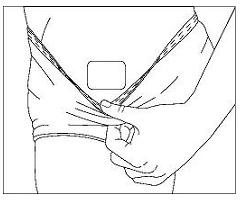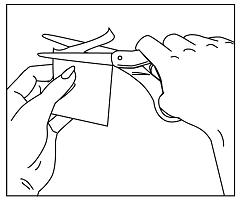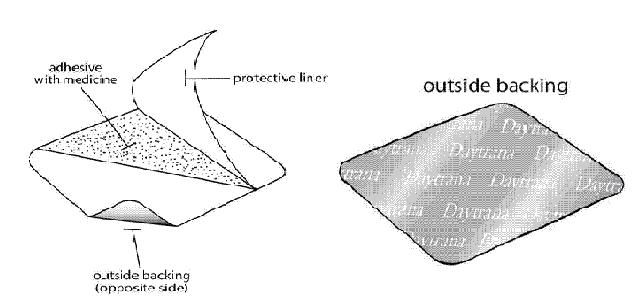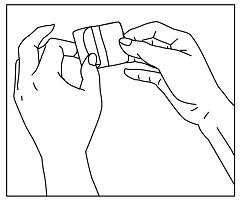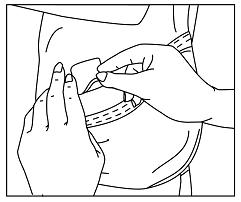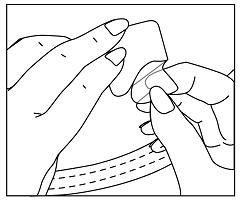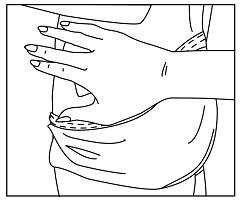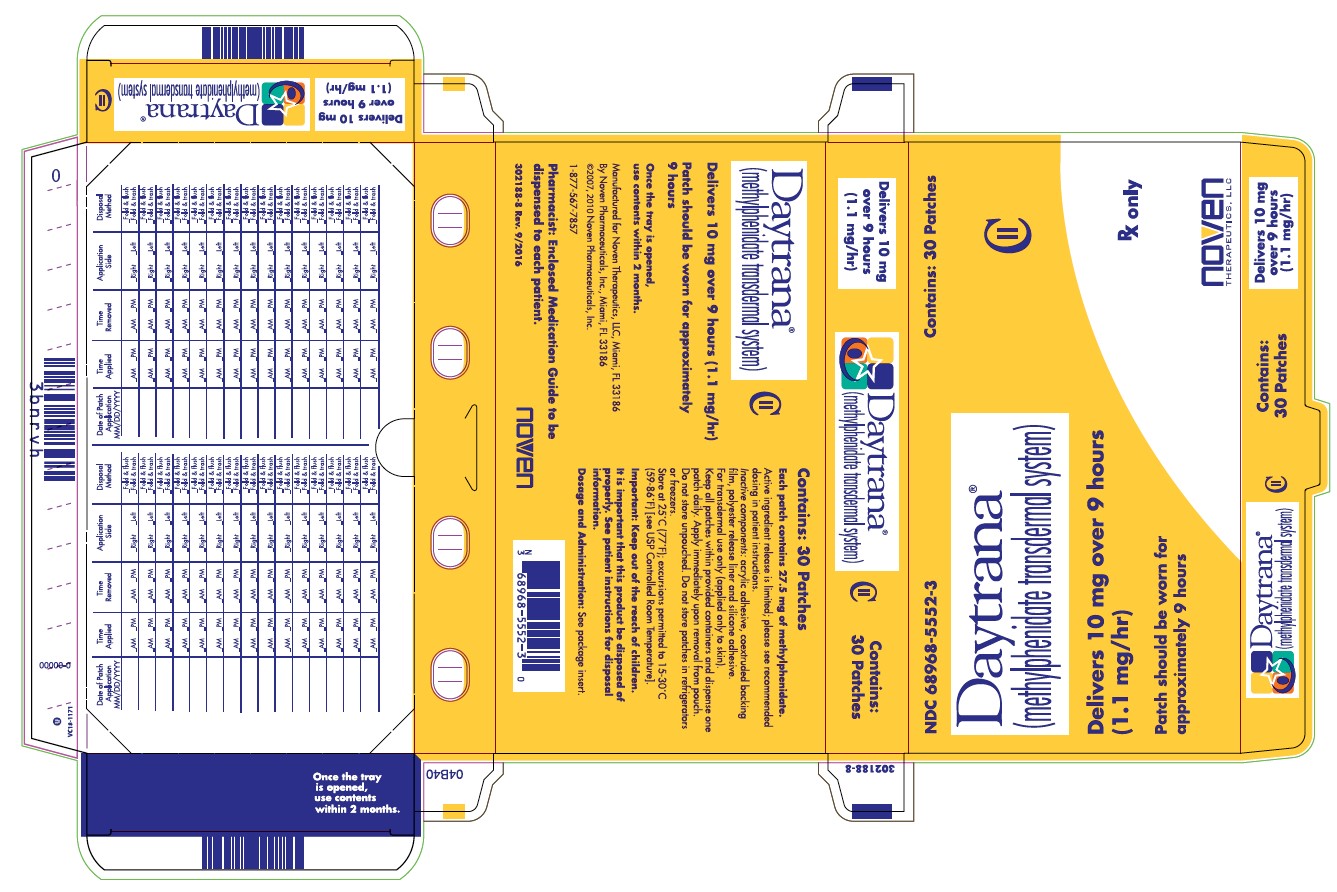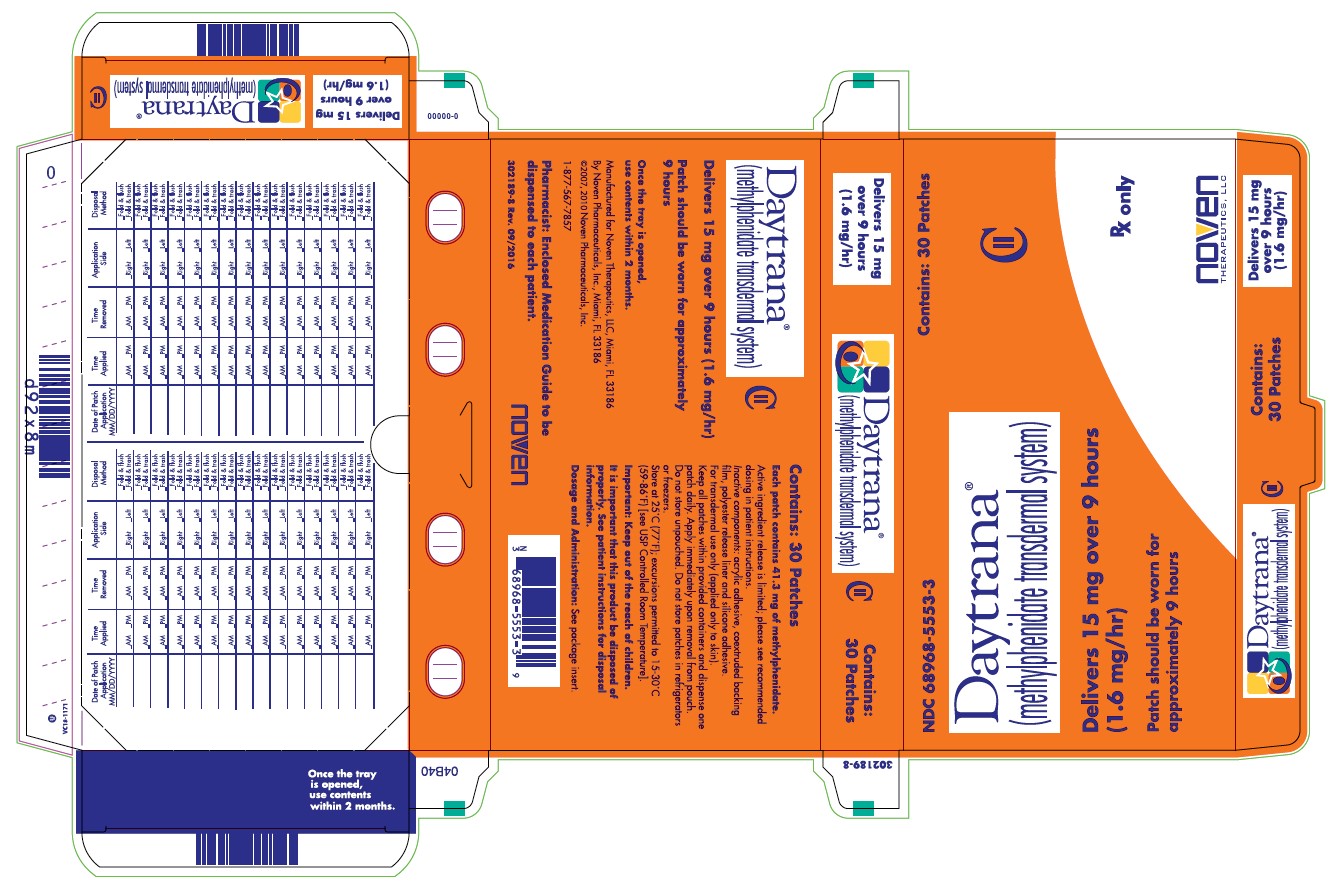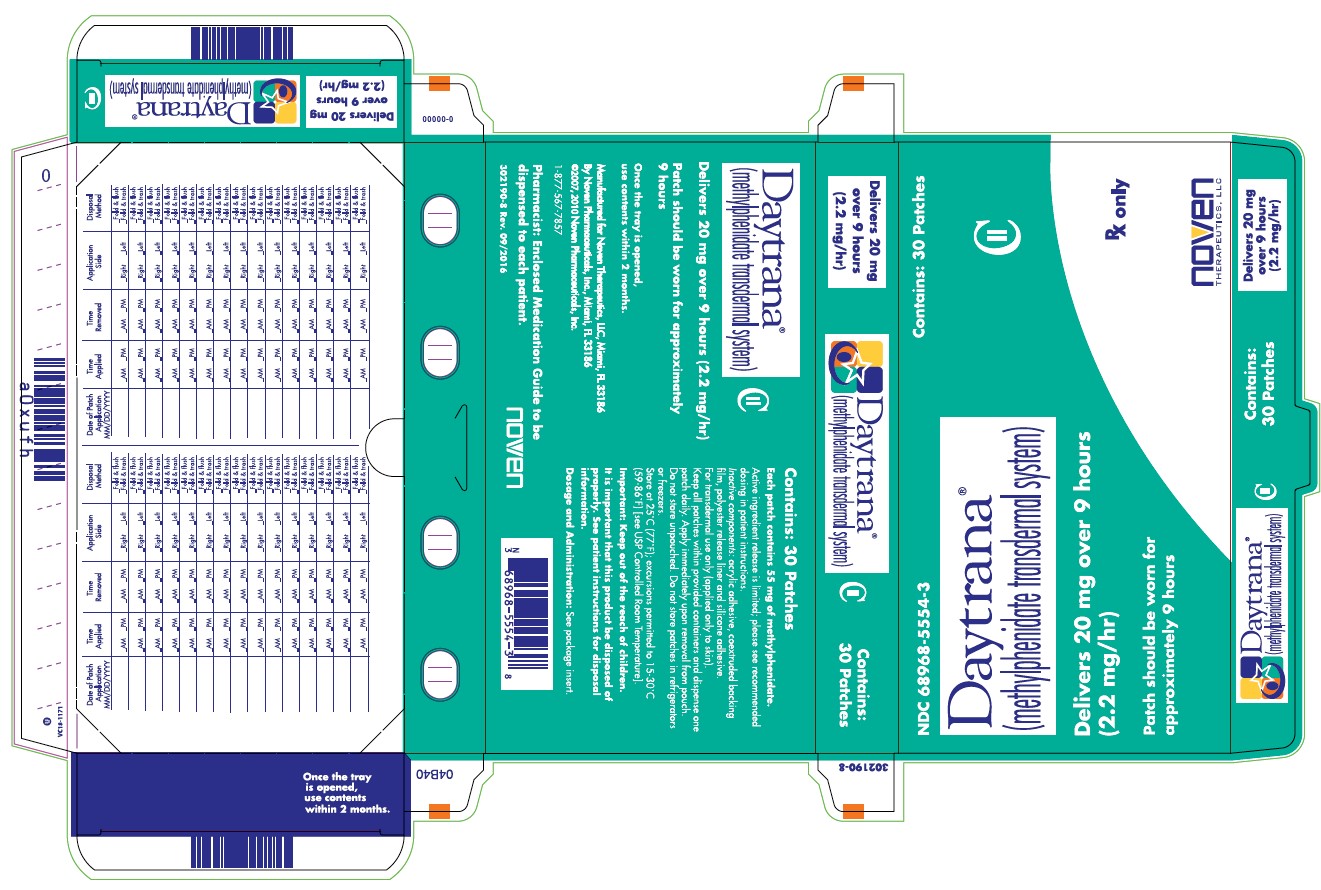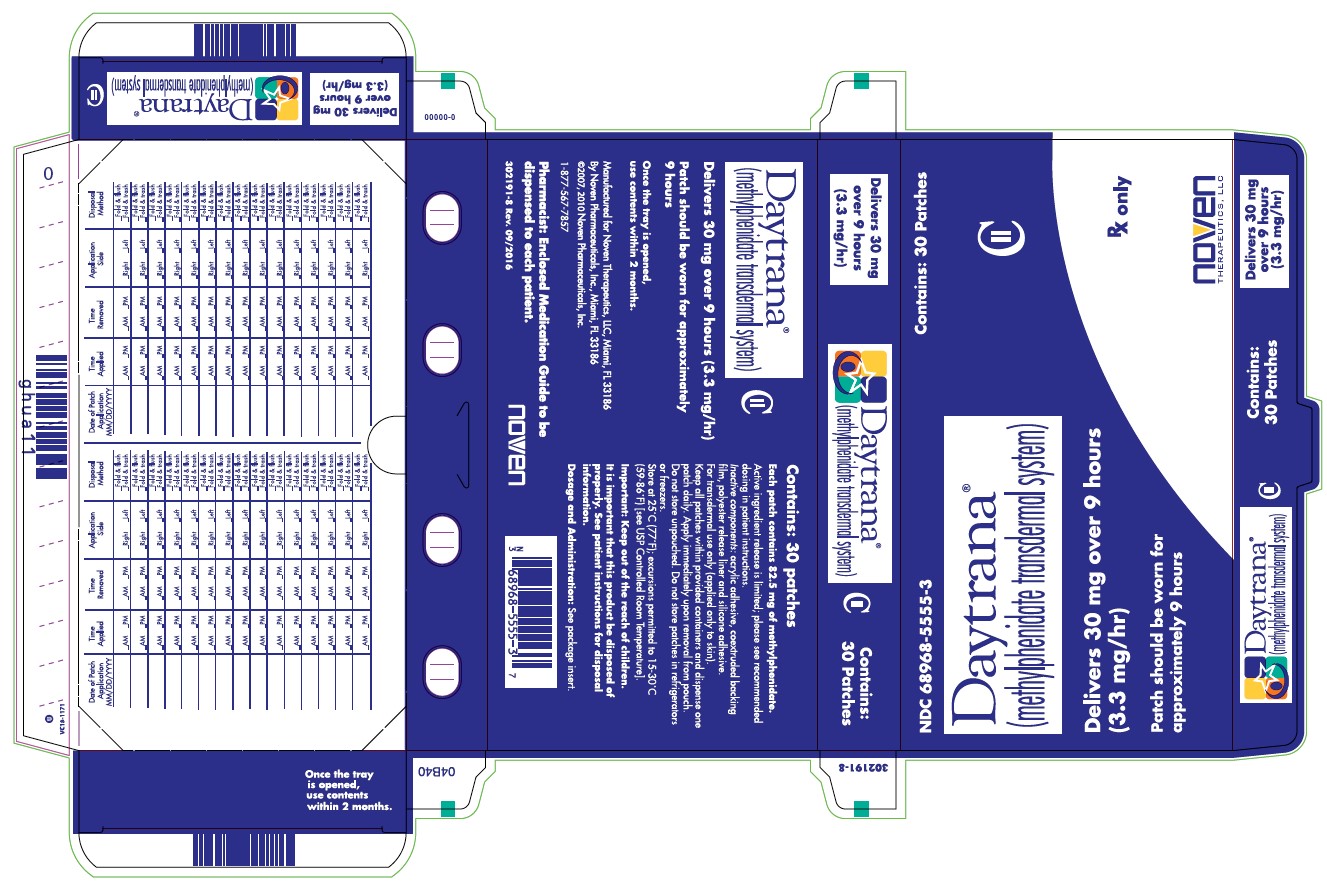 DRUG LABEL: Daytrana

NDC: 68968-5552 | Form: PATCH
Manufacturer: Noven Therapeutics, LLC
Category: prescription | Type: HUMAN PRESCRIPTION DRUG LABEL
Date: 20250901
DEA Schedule: CII

ACTIVE INGREDIENTS: METHYLPHENIDATE 10 mg/9 h

HIGHLIGHTS OF PRESCRIBING INFORMATION

These highlights do not include all the information needed to use DAYTRANA® safely and effectively. See full prescribing information for DAYTRANA.
DAYTRANA® (methylphenidate transdermal system), CII
Initial U.S. Approval: 2006

WARNING: ABUSE, MISUSE, AND ADDICTION

See full prescribing information for complete boxed warning

DAYTRANA has high potential for abuse and misuse, which can lead to the development of a substance use disorder, including addiction. Misuse and abuse of CNS stimulants, including DAYTRANA, can result in overdose and death (5.1, 9.2, 10):

- Before prescribing DAYTRANA, assess each patient’s risk for abuse, misuse, and addiction.
- Educate patients and their families about these risks, proper storage of the drug, and proper disposal of any unused drug.
- Throughout treatment, reassess each patient’s risk and frequently monitor for signs and symptoms of abuse, misuse, and addiction.

RECENT MAJOR CHANGES

Indications and Usage (1) | 09/2025
Warnings and Precautions (5.8) | 09/2025

1 INDICATIONS AND USAGE

DAYTRANA is a central nervous system (CNS) stimulant indicated for the treatment of Attention Deficit Hyperactivity Disorder (ADHD) in pediatric patients 6 to 17 years of age. (1)

Limitations of Use
The use of DAYTRANA is not recommended in pediatric patients younger than 6 years of age because they had higher plasma exposure and a higher incidence of adverse reactions (e.g., weight loss) than patients 6 years and older at the same dosage (5.8, 8.4).

2 DOSAGE AND ADMINISTRATION

- The recommended starting dose for patients new to or converting from another formulation of methylphenidate is 10 mg. (2.2)
- DAYTRANA should be applied to the hip area (using alternating sites) 2 hours before an effect is needed and should be removed 9 hours after application. DAYTRANA may be removed earlier than 9 hours if a shorter duration of effect is desired or late day side effects appear. (2.2, 2.3)
- Dosage should be titrated to effect. Dose titration, final dosage, and wear time should be individualized according to the needs and response of the patient. (2.2)

3 DOSAGE FORM AND STRENGTHS

Transdermal system: 10mg/9 hours (1.1 mg/hr), 15mg/9 hours (1.6 mg/hr), 20mg/9 hours (2.2 mg/hr), 30mg/9 hours (3.3 mg/hr) (3)

4 CONTRAINDICATIONS

- Known hypersensitivity to methylphenidate (4.1)
- Patients currently using or within 2 weeks of using an MAO inhibitor (4.2)

5 WARNINGS AND PRECAUTIONS

- Risks to Patients with Serious Cardiac Disease: Avoid use in patients with known structural cardiac abnormalities, cardiomyopathy, serious cardiac arrhythmias, coronary artery disease, or other serious cardiac disease. (5.2)
- Increased Blood Pressure and Heart Rate: Monitor blood pressure and pulse. (5.3)
- Psychiatric Adverse Reactions: Prior to initiating DAYTRANA, screen patients for risk factors for developing a manic episode. If new psychotic or manic symptoms occur, consider discontinuing DAYTRANA. (5.4)
- Seizures: Stimulants may lower the convulsive threshold. Discontinue in the presence of seizures. (5.5)
- Priapism: If abnormally sustained or frequent and painful erections occur, patients should seek immediate medical attention. (5.6)
- Peripheral Vasculopathy, including Raynaud’s phenomenon: Careful observation for digital changes is necessary during DAYTRANA treatment. Further clinical evaluation (e.g., rheumatology referral) may be appropriate for patients who develop signs or symptoms of peripheral vasculopathy. (5.7)
- Long-Term Suppression of Growth in Pediatric Patients: Closely monitor (height and weight) in pediatric patients. Pediatric patients not growing or gaining height or weight as expected may need to have their treatment interrupted. (5.8)
- Chemical Leukoderma: DAYTRANA use may result in a persistent loss of skin pigmentation at and around the application site. Loss of pigmentation, in some cases, has been reported at other sites distant from the application site. Monitor for signs of skin depigmentation. Discontinue DAYTRANA if it occurs. (5.9)
- Contact Sensitization: Use of DAYTRANA may lead to contact sensitization. Treatment should be discontinued if contact sensitization is suspected. Erythema is commonly seen with use of DAYTRANA and is not by itself an indication of sensitization. However, contact sensitization should be suspected if erythema is accompanied by evidence of a more intense local reaction (edema, papules, vesicles) that does not significantly improve within 48 hours or spreads beyond the transdermal system site. (5.10)
- External Heat: Patients should be advised to avoid exposing the DAYTRANA application site to direct external heat sources. When heat is applied to DAYTRANA after application, both the rate and extent of absorption are significantly increased. (5.11)
- Hematologic monitoring: Periodic CBC, differential, and platelet counts are advised during prolonged therapy. (5.12)
- Acute Angle Closure Glaucoma: DAYTRANA-treated patients considered at risk for acute angle closure glaucoma (e.g., patients with significant hyperopia) should be evaluated by an ophthalmologist. (5.13)
- Increased Intraocular Pressure (IOP) and Glaucoma: Prescribe DAYTRANA to patients with open-angle glaucoma or abnormally increased IOP only if the benefit of treatment is considered to outweigh the risk. Closely monitor patients with a history of increased IOP or open angle glaucoma. (5.14)
- Motor and Verbal Tics and Worsening of Tourette’s Syndrome: Before initiating DAYTRANA, assess the family history and clinically evaluate patients for tics or Tourette’s syndrome. Regularly monitor patients for the emergence or worsening of tics or Tourette’s syndrome. Discontinue treatment if clinically appropriate. (5.15)

6 ADVERSE REACTIONS

- Pediatric patients (ages 6 to 12 years): The most commonly (≥5% and twice the rate of placebo) reported adverse reactions in pediatric patients ages 6 to 12 years included appetite decreased, insomnia, nausea, vomiting, weight decreased, tic, affect lability, and anorexia. (6.1)
- Pediatric patients (ages 13 to 17 years): The most commonly (≥5% and twice the rate of placebo) reported adverse reactions in pediatric patients ages 13 to 17 years included appetite decreased, nausea, insomnia, weight decreased, dizziness, abdominal pain, and anorexia. The majority of subjects in these trials had erythema at the application site. (6.1)

To report SUSPECTED ADVERSE REACTIONS, contact Noven Therapeutics, LLC at 1-800-455-8070 or FDA at 1-800-FDA-1088 or www.fda.gov/medwatch.

7 DRUG INTERACTIONS

- Antihypertensive Drugs: Monitor blood pressure. Adjust dosage of antihypertensive drug as needed. (7.2)

FULL PRESCRIBING INFORMATION

WARNING: ABUSE, MISUSE, AND ADDICTION

DAYTRANA has a high potential for abuse and misuse, which can lead to the development of substance use disorder, including addiction. Misuse and abuse of CNS stimulants, including DAYTRANA, can result in overdose and death [see Overdosage (10)] , and this risk is increased with higher doses or unapproved methods of administration, such as snorting or injection.

Before prescribing DAYTRANA, assess each patient’s risk for abuse, misuse, and addiction. Educate patients and their families about these risks, proper storage of the drug, and proper disposal of any unused drug. Throughout DAYTRANA treatment, reassess each patient’s risk of abuse, misuse, and addiction and frequently monitor for signs and symptoms of abuse, misuse, and addiction [see Warnings and Precautions (5.1) and Drug Abuse and Dependence (9.2)] .

1 INDICATIONS AND USAGE

DAYTRANA (methylphenidate transdermal system) is indicated for the treatment of Attention Deficit Hyperactivity Disorder (ADHD) in pediatric patients 6 to 17 years of age.

Limitations of Use

The use of DAYTRANA is not recommended in pediatric patients younger than 6 years of age because they had higher plasma exposure and a higher incidence of adverse reactions (e.g., weight loss) than patients 6 years and older at the same dosage [see Warnings and Precautions (5.8), Use in Specific Populations (8.4)].

2 DOSAGE AND ADMINISTRATION

2.1 Pretreatment Screening

Prior to treating patients with DAYTRANA, assess:

- for the presence of cardiac disease (i.e., perform a careful history, family history of sudden death or ventricular arrhythmia, and physical exam) [see Warnings and Precautions (5.2)] .
- the family history and clinically evaluate patients for motor or verbal tics or Tourette’s syndrome before initiating DAYTRANA [see Warnings and Precautions (5.15)] .

2.2 Recommended Dosage

It is recommended that DAYTRANA be applied to the hip area 2 hours before an effect is needed and should be removed 9 hours after application. Dosage should be titrated to effect. The recommended dose titration schedule is shown in the table below. Dose titration, final dosage, and wear time should be individualized according to the needs and response of the patient.

Table 1 DAYTRANA - Recommended Titration Schedule (Patients New to Methylphenidate)
Upward Titration, if Response is Not Maximized
 | Week 1 | Week 2 | Week 3 | Week 4
Transdermal System Size | 12.5 cm ^2 | 18.75 cm ^2 | 25 cm ^2 | 37.5 cm ^2
Nominal Delivered Dose* (mg/9 hours) | 10 mg | 15 mg | 20 mg | 30 mg
Delivery Rate* | (1.1 mg/hr)* | (1.6 mg/hr)* | (2.2 mg/hr)* | (3.3 mg/hr)*
*Nominal in vivo delivery rate in children and adolescents when applied to the hip, based on a 9-hour wear period.

Patients converting from another formulation of methylphenidate should follow the above titration schedule due to differences in bioavailability of DAYTRANA compared to other products.

2.3 Application

The parent or caregiver should be encouraged to use the administration chart included with each carton of DAYTRANA to monitor application and removal time, and method of disposal. It is recommended that parents or caregivers apply and remove the transdermal system for children; responsible adolescents may apply or remove the transdermal system themselves if appropriate. If a transdermal system was removed without the parent or caregiver's knowledge, or if a transdermal system is missing from the tray, the parent or caregiver should be encouraged to ask the child when and how the transdermal system was removed. The Medication Guide includes a timetable to calculate when to remove DAYTRANA, based on the 9-hour application time.

The adhesive side of DAYTRANA should be placed on a clean, dry area of the hip. The area selected should not be oily, damaged, or irritated. Apply DAYTRANA to the hip area avoiding the waistline, since clothing may cause the transdermal system to rub off. When applying the transdermal system the next morning, place on the opposite hip at a new site if possible.

If patients or caregivers experience difficulty separating the transdermal system from the release liner or observe transfer of adhesive to the liner, tearing and/or other damage to the transdermal system during removal from the liner, the transdermal system should be discarded and a new transdermal system should be applied. Patients or caregivers should inspect the release liner to ensure that no adhesive containing medication has transferred to the liner. If adhesive transfer has occurred, the transdermal system should be discarded. Refer to the Instructions for Use for recommendations for discarding used DAYTRANA.

DAYTRANA should be applied immediately after opening the individual pouch and removing the protective liner. Do not use if the individual pouch seal is broken or if the transdermal system appears to be damaged. Do not cut transdermal systems. Only intact transdermal systems should be applied. The transdermal system should then be pressed firmly in place with the palm of the hand for approximately 30 seconds, making sure that there is good contact of the transdermal system with the skin, especially around the edges. Exposure to water during bathing, swimming, or showering can affect transdermal system adherence. DAYTRANA should not be applied or re-applied with dressings, tape, or other common adhesives. In the event that a transdermal system does not fully adhere to the skin upon application, or becomes partially or fully detached during wear time, the transdermal system should be discarded and a new transdermal system may be applied at a different site. The total recommended wear time for that day should remain 9 hours regardless of the number of transdermal systems used.

All patients should be advised to avoid exposing the DAYTRANA application site to direct external heat sources, such as hair dryers, heating pads, electric blankets, heated water beds, etc., while wearing the transdermal system [see Warnings and Precautions (5.10)]. When heat is applied to DAYTRANA after transdermal system application, both the rate and the extent of absorption are significantly increased. The temperature-dependent increase in methylphenidate absorption can be greater than 2-fold [see Clinical Pharmacology (12.3)]. This increased absorption can be clinically significant and result in overdose of methylphenidate [see Overdosage (10)].

DAYTRANA should not be stored in refrigerators or freezers.

2.4 Removal of DAYTRANA

DAYTRANA should be peeled off slowly. If necessary, transdermal system removal may be facilitated by gently applying an oil-based product (i.e., petroleum jelly, olive oil, or mineral oil) to the transdermal system edges, gently working the oil underneath the transdermal system edges. If any adhesive remains on the skin following transdermal system removal, an oil-based product may be applied to transdermal system sites in an effort to gently loosen and remove any residual adhesive that remains following transdermal system removal.

In the unlikely event that a transdermal system remains tightly adhered despite these measures, the patient or caregiver should contact the physician or pharmacist. Nonmedical adhesive removers and acetone-based products (i.e., nail polish remover) should not be used to remove DAYTRANA or adhesive.

2.5 Dose/Wear Time Reduction and Discontinuation

DAYTRANA may be removed earlier than 9 hours if a shorter duration of effect is desired or late day side effects appear. Plasma concentrations of d-methylphenidate generally begin declining when the transdermal system is removed, although absorption may continue for several hours. Individualization of wear time may help manage some of the side effects caused by methylphenidate. If aggravation of symptoms or other adverse events occur, the dosage or wear time should be reduced, or, if necessary, the drug should be discontinued. Residual methylphenidate remains in used transdermal systems when worn as recommended.

3 DOSAGE FORM AND STRENGTHS

Four dosage strengths are available:

Nominal Dose Delivered (mg) Over 9 Hours* | Dosage Rate* (mg/hr) | Transdermal System Size (cm ^2) | Methylphenidate Content per Transdermal System (mg)
10 | 1.1 | 12.5 | 27.5
15 | 1.6 | 18.75 | 41.3
20 | 2.2 | 25 | 55
30 | 3.3 | 37.5 | 82.5
*Nominal in vivo delivery rate in children and adolescents when applied to the hip, based on a 9-hour wear period.

4 CONTRAINDICATIONS

4.1 Hypersensitivity to Methylphenidate

DAYTRANA is contraindicated in patients known to be hypersensitive to methylphenidate or other components of the product (polyester/ethylene vinyl acetate laminate film backing, acrylic adhesive, silicone adhesive, and fluoropolymer-coated polyester) [see Description (11)] .

4.2 Monoamine Oxidase Inhibitors

DAYTRANA is contraindicated during treatment with monoamine oxidase inhibitors, and within a minimum of 14 days following discontinuation of treatment with a monoamine oxidase inhibitor (hypertensive crises may result).

5 WARNINGS AND PRECAUTIONS

5.1 Abuse, Misuse, and Addiction

DAYTRANA has a high potential for abuse and misuse. The use of DAYTRANA exposes individuals to the risks of abuse and misuse, which can lead to the development of a substance use disorder, including addiction. DAYTRANA can be diverted for non-medical use into illicit channels or distribution [see Drug Abuse and Dependence (9.2)]. Misuse and abuse of CNS stimulants, including DAYTRANA, can result in overdose and death [see Overdosage (10)] , and this risk is increased with higher doses or unapproved methods of administration, such as snorting or injection.

Before prescribing DAYTRANA, assess each patient’s risk for abuse, misuse, and addiction. Educate patients and their caregivers or families about these risks. Advise patients to store DAYTRANA in a safe place, preferably locked, and instruct patients to not give DAYTRANA to anyone else. Throughout DAYTRANA treatment, reassess each patient’s risk of abuse, misuse, and addiction and frequently monitor for signs and symptoms of abuse, misuse, and addiction.

DAYTRANA has special disposal instructions. Instruct patients to find a take back location to dispose of unused or expired DAYTRANA. If a take back program is unavailable, instruct them to:

1. Remove DAYTRANA from its pouch, separate it from its liner, fold it in half with the adhesive sides touching each other, and immediately flush the used transdermal system down the toilet, and
2. Place the pouch and liner in a container, close the container, and throw out the container in the trash (advise patients not to flush the pouch and liner down the toilet).

5.2 Risks to Patients with Serious Cardiac Disease

Sudden death has been reported in patients with structural cardiac abnormalities or other serious cardiac disease who were treated with CNS stimulants at the recommended ADHD dosage.

Avoid DAYTRANA use in patients with known structural cardiac abnormalities, cardiomyopathy, serious cardiac arrhythmia, coronary artery disease, or other serious cardiac disease.

5.3 Increased Blood Pressure and Heart Rate

CNS stimulants may cause an increase in blood pressure (mean increase approximately 2 to 4 mmHg) and heart rate (mean increase approximately 3 to 6 bpm). Some patients may have larger increases.

Monitor all DAYTRANA-treated patients for hypertension and tachycardia.

5.4 Psychiatric Adverse Reactions

Exacerbation of Pre-Existing Psychosis

CNS stimulants may exacerbate symptoms of behavior disturbance and thought disorder in patients with a pre-existing psychotic disorder.

Induction of a Manic Episode in Patients with Bipolar Disease

CNS stimulants may induce a manic or mixed episode in patients. Prior to initiating DAYTRANA treatment, screen patients for risk factors for developing a manic episode (e.g., comorbid or history of depressive symptoms or a family history of suicide, bipolar disorder, or depression).

New Psychotic or Manic Symptoms

CNS stimulants, at the recommended dosages, may cause psychotic or manic symptoms, (e.g., hallucinations, delusional thinking, or mania) in patients without a prior history of psychotic illness or mania. In a pooled analysis of multiple short-term, placebo-controlled studies of CNS stimulants, psychotic or manic symptoms occurred in approximately 0.1% of CNS stimulant-treated patients compared with 0% of placebo-treated patients. If such symptoms occur, consider discontinuing DAYTRANA.

5.5 Seizures

There is some clinical evidence that stimulants may lower the convulsive threshold in patients with prior history of seizures, in patients with prior EEG abnormalities in absence of seizures, and, very rarely, in patients without a history of seizures and no prior EEG evidence of seizures. In the presence of seizures, the drug should be discontinued.

5.6 Priapism

Prolonged and painful erections, sometimes requiring surgical intervention, have been reported with methylphenidate use in both adult and pediatric male patients. Although priapism was not reported with methylphenidate initiation, it developed after some time on the methylphenidate, often subsequent to an increase in dosage. Priapism also occurred during methylphenidate withdrawal (drug holidays or during discontinuation).

DAYTRANA-treated patients who develop abnormally sustained or frequent and painful erections should seek immediate medical attention.

5.7 Peripheral Vasculopathy, including Raynaud’s phenomenon

Stimulant medications, including DAYTRANA, used to treat ADHD are associated with peripheral vasculopathy, including Raynaud’s phenomenon. Signs and symptoms are usually intermittent and mild; however, sequelae have included digital ulceration and/or soft tissue breakdown. Effects of peripheral vasculopathy, including Raynaud’s phenomenon, were observed in post-marketing reports and at therapeutic dosages of CNS stimulants in all age groups throughout the course of treatment. Signs and symptoms generally improved after dosage reduction or discontinuation of the CNS stimulant.

Careful observation for digital changes is necessary during DAYTRANA treatment. Further clinical evaluation (e.g., rheumatology referral) may be appropriate for DAYTRANA-treated patients who develop signs or symptoms of peripheral vasculopathy.

5.8 Long-Term Suppression of Growth in Pediatric Patients

DAYTRANA is not approved for use and is not recommended in pediatric patients below 6 years of age [see Use in Specific Populations (8.4)].

CNS stimulants have been associated with weight loss and slowing of growth rate in pediatric patients.

Careful follow-up of weight and height in children ages 7 to 10 years who were randomized to either methylphenidate or non-medication treatment groups over 14 months, as well as in naturalistic subgroups of newly methylphenidate-treated and non-medication treated children over 36 months (to the ages of 10 to 13 years), suggests that pediatric patients who received methylphenidate for 7 days per week throughout the year had a temporary slowing in growth rate (on average, a total of about 2 cm less growth in height and 2.7 kg less growth in weight over 3 years), without evidence of growth rebound during this development period.

Closely monitor growth (weight and height) in DAYTRANA-treated pediatric patients. Pediatric patients not growing or gaining height or weight as expected may need to have their treatment interrupted.

5.9 Chemical Leukoderma

DAYTRANA use may result in a persistent loss of skin pigmentation at and around the application site. Loss of pigmentation, in some cases, has been reported at other sites distant from the application site. Chemical leukoderma can mimic the appearance of vitiligo, particularly when the loss of skin pigmentation involves areas distant from the application site. Individuals with a history of vitiligo and/or a family history of vitiligo may be more at risk. Skin depigmentation may persist even after DAYTRANA use is discontinued. Monitor for signs of skin depigmentation, and advise patients to immediately inform their healthcare provider if changes in skin pigmentation occur. Discontinue use of the DAYTRANA in patients with chemical leukoderma.

5.10 Contact Sensitization

In an open-label study of 305 subjects conducted to characterize dermal reactions in children with ADHD treated with DAYTRANA using a 9-hour wear time, one subject (0.3%) was confirmed by patch testing to be sensitized to methylphenidate (allergic contact dermatitis). This subject experienced erythema and edema at DAYTRANA application sites with concurrent urticarial lesions on the abdomen and legs resulting in treatment discontinuation. This subject was not transitioned to oral methylphenidate.

Use of DAYTRANA may lead to contact sensitization. DAYTRANA should be discontinued if contact sensitization is suspected. Erythema is commonly seen with use of DAYTRANA and is not by itself an indication of sensitization. However, contact sensitization should be suspected if erythema is accompanied by evidence of a more intense local reaction (edema, papules, vesicles) that does not significantly improve within 48 hours or spreads beyond the transdermal system site. Confirmation of a diagnosis of contact sensitization (allergic contact dermatitis) may require further diagnostic testing.

Patients sensitized from use of DAYTRANA, as evidenced by development of an allergic contact dermatitis, may develop systemic sensitization or other systemic reactions if methylphenidate-containing products are taken via other routes, e.g., orally. Manifestations of systemic sensitization may include a flare-up of previous dermatitis or of prior positive patch-test sites, or generalized skin eruptions in previously unaffected skin. Other systemic reactions may include headache, fever, malaise, arthralgia, diarrhea, or vomiting. No cases of systemic sensitization have been observed in clinical trials of DAYTRANA.

Patients who develop contact sensitization to DAYTRANA and require oral treatment with methylphenidate should be initiated on oral medication under close medical supervision. It is possible that some patients sensitized to methylphenidate by exposure to DAYTRANA may not be able to take methylphenidate in any form.

5.11 Patients Using External Heat

Patients should be advised to avoid exposing the DAYTRANA application site to direct external heat sources, such as hair dryers, heating pads, electric blankets, heated water beds, etc., while wearing the transdermal system. When heat is applied to DAYTRANA after application, both the rate and extent of absorption are significantly increased. The temperature-dependent increase in methylphenidate absorption can be greater than 2-fold [see Clinical Pharmacology (12.3)]. This increased absorption can be clinically significant and can result in overdose of methylphenidate [see Overdosage (10)].

5.12 Hematologic Monitoring

Periodic CBC, differential, and platelet counts are advised during prolonged therapy.

5.13 Acute Angle Closure Glaucoma

There have been reports of angle closure glaucoma associated with methylphenidate treatment.

Although the mechanism is not clear, DAYTRANA-treated patients considered at risk for acute angle closure glaucoma (e.g., patients with significant hyperopia) should be evaluated by an ophthalmologist.

5.14 Increased Intraocular Pressure and Glaucoma

There have been reports of an elevation of intraocular pressure (IOP) associated with methylphenidate treatment [see Adverse Reactions (6.2)] .

Prescribe DAYTRANA to patients with open-angle glaucoma or abnormally increased IOP only if the benefit of treatment is considered to outweigh the risk. Closely monitor DAYTRANA-treated patients with a history of abnormally increased IOP or open angle glaucoma.

5.15 Motor and Verbal Tics, and Worsening of Tourette’s Syndrome

CNS stimulants, including methylphenidate, have been associated with the onset or exacerbation of motor and verbal tics. Worsening of Tourette’s syndrome has also been reported [see Adverse Reactions (6.2)] .

Before initiating DAYTRANA, assess the family history and clinically evaluate patients for tics or Tourette’s syndrome. Regularly monitor DAYTRANA-treated patients for the emergence or worsening of tics or Tourette’s syndrome, and discontinue treatment if clinically appropriate.

6 ADVERSE REACTIONS

Detailed information on serious and adverse reactions of particular importance is provided in the Boxed Warning and Warnings and Precautions (5) sections:

- Abuse, Misuse, and Addiction [see Boxed Warning]
- Hypersensitivity to Methylphenidate [see Contraindications (4.1)]
- Monoamine Oxidase Inhibitors [see Contraindications (4.2) and Drug Interactions (7.1)]
- Risks to Patients with Serious Cardiac Disease [see Warnings and Precautions (5.2)]
- Increased Blood Pressure and Heart Rate [see Warnings and Precautions (5.3)]
- Psychiatric Adverse Reactions [see Warnings and Precautions (5.4)]
- Seizures [see Warnings and Precautions (5.5)]
- Priapism [see Warnings and Precautions (5.6)]
- Peripheral Vasculopathy [see Warnings and Precautions (5.7)]
- Long-Term Suppression of Growth in Pediatric Patients [see Warnings and Precautions (5.8)]
- Chemical Leukoderma [see Warnings and Precautions (5.9)]
- Contact Sensitization [see Warnings and Precautions (5.10)]
- External Heat [see Warnings and Precautions (5.11)]
- Hematologic Monitoring [see Warnings and Precautions (5.12)]
- Acute Angle Closure Glaucoma [see Warnings and Precautions (5.13)]
- Increased Intraocular Pressure and Glaucoma [see Warnings and Precautions (5.14)]
- Motor and Verbal Tics, and Worsening of Tourette’s Syndrome [see Warnings and Precautions (5.15)]

6.1 Clinical Trials Experience

Because clinical trials are conducted under widely varying conditions, adverse reactions rates observed in the clinical trials of a drug cannot be directly compared to rates in the clinical trials of another drug and may not reflect the rates observed in practice.

The most commonly reported (frequency ≥ 5% and twice the rate of placebo) adverse reactions in a controlled trial in children aged 6-12 included appetite decreased, insomnia, nausea, vomiting, weight decreased, tic, affect lability, and anorexia. The most commonly reported (frequency ≥ 5% and twice the rate of placebo) adverse reactions in a controlled trial in adolescents aged 13-17 were appetite decreased, nausea, insomnia, weight decreased, dizziness, abdominal pain, and anorexia [see Adverse Reactions (6.1)].

The most common (≥ 2% of subjects) adverse reaction associated with discontinuations in double-blind clinical trials in children or adolescents was application site reactions [see Adverse Reactions (6.1)].

The overall DAYTRANA development program included exposure to DAYTRANA in a total of 2,152 participants in clinical trials, including 1,529 children aged 6-12, 223 adolescents aged 13-17, and 400 adults. The 1,752 child and adolescent subjects aged 6-17 years were evaluated in 10 controlled clinical studies, 7 open-label clinical studies, and 5 clinical pharmacology studies. In a combined studies pool of children using DAYTRANA with a wear time of 9 hours, 212 subjects were exposed for ≥ 6 months and 115 were exposed for ≥ 1 year; 85 adolescents were exposed for ≥ 6 months. Most patients studied were exposed to DAYTRANA transdermal system sizes of 12.5 cm^2, 18.75 cm^2, 25 cm^2 or 37.5 cm^2, with a wear time of 9 hours.

In the data presented below, the adverse reactions reported during exposure were obtained primarily by general inquiry at each visit, and were recorded by the clinical investigators using terminology of their own choosing. Consequently, it is not possible to provide a meaningful estimate of the proportion of individuals experiencing adverse reactions without first grouping similar types of events into a smaller number of standardized event categories.

Adverse Reactions in Clinical Studies with Discontinuation of Treatment

In a 7-week double-blind, parallel-group, placebo-controlled study in children with ADHD conducted in the outpatient setting, 7.1% (7/98) of patients treated with DAYTRANA discontinued due to adverse events compared with 1.2% (1/85) receiving placebo. The most commonly reported (≥ 1% and twice the rate of placebo) adverse reactions leading to discontinuation in the DAYTRANA group were application site reaction (2%), tics (1%), headache (1%), and irritability (1%).

In a 7-week double-blind, parallel-group, placebo-controlled study in adolescents with ADHD conducted in the outpatient setting, 5.5% (8/145) of patients treated with DAYTRANA discontinued due to adverse reactions compared with 2.8% (2/72) receiving placebo. The most commonly reported adverse reactions leading to discontinuation in the DAYTRANA group were application site reaction (2%) and decreased appetite/anorexia (1.4%).

Commonly Observed Adverse Reactions in Double-Blind, Placebo-Controlled Trials

Skin Irritation and Application Site Reactions

DAYTRANA is a dermal irritant. In addition to the most commonly reported adverse reactions presented in Table 2, the majority of subjects in those studies had minimal to definite skin erythema at the DAYTRANA application site. This erythema generally caused no or minimal discomfort and did not usually interfere with therapy or result in discontinuation from treatment. Erythema is not by itself a manifestation of contact sensitization. However, contact sensitization should be suspected if erythema is accompanied by evidence of a more intense local reaction (edema, papules, vesicles) that does not significantly improve within 48 hours or spreads beyond the transdermal system site [see Warnings and Precautions (5.10)].

Most Commonly Reported Adverse Reactions

Table 2 lists treatment-emergent adverse reactions reported in ≥ 1% DAYTRANA-treated children or adolescents with ADHD in two 7 week double-blind, parallel-group, placebo-controlled studies conducted in the outpatient setting. Overall, in these studies, 75.5% of children and 78.6% of adolescents experienced at least 1 adverse event.

Table 2 Number (%) of Subjects with Commonly Reported Adverse Reactions (≥ 1% in the DAYTRANA Group) in 7-Week Placebo-controlled Studies in Either Children or Adolescents - Safety Population
 | Adolescents |  | Children
System Organ Class Preferred term | Placebo N = 72 | DAYTRANA N = 145 | Placebo N = 85 | DAYTRANA N = 98
Cardiac Disorders
Tachycardia | 0 (0) | 1 (0.7) | 0 (0) | 1 (1.0)
Gastrointestinal disorders
Abdominal pain | 0 (0) | 7 (4.8) | 5 (5.9) | 7 (7.1)
Nausea | 2 (2.8) | 14 (9.7) | 2 (2.4) | 12 (12.2)
Vomiting | 1 (1.4) | 5 (3.4) | 4 (4.7) | 10 (10.2)
Investigations
Weight decreased | 1 (1.4) | 8 (5.5) | 0 (0) | 9 (9.2)
Metabolism and nutrition disorders
Anorexia | 1 (1.4) | 7 (4.8) | 1 (1.2) | 5 (5.1)
Decreased appetite | 1 (1.4) | 37 (25.5) | 4 (4.7) | 25 (25.5)
Nervous system disorders
Dizziness | 1 (1.4) | 8 (5.5) | 1 (1.2) | 0 (0)
Headache | 9 (12.5) | 18 (12.4) | 10 (11.8) | 15 (15.3)
Psychiatric disorders
Affect lability | 1 (1.4) | 0 (0) | 0 (0) | 6 (6.1)*
Insomnia | 2 (2.8) | 9 (6.2) | 4 (4.7) | 13 (13.3)
Irritability | 5 (6.9) | 16 (11) | 4 (4.7) | 7 (7.1)
Tic | 0 (0) | 0 (0) | 0 (0) | 7 (7.1)
* Six subjects had affect lability, all judged as mild and described as increased emotionally sensitive, emotionality, emotional instability, emotional lability, and intermittent emotional

Adverse Reactions in Studies with the Long-Term Use of DAYTRANA

In a long-term open-label study of up to 12 months duration in 326 children wearing DAYTRANA 9 hours daily, the most common (≥ 10%) adverse reactions were decreased appetite, headache, and weight decreased. A total of 30 subjects (9.2%) were withdrawn from the study due to adverse events and 22 additional subjects (6.7%) discontinued treatment as the result of an application site reaction. Other than application site reactions, affect lability (5 subjects, 1.5%) was the only additional adverse reaction leading to discontinuation reported with a frequency of greater than 1%.

In a long-term open-label study of up to 6 months duration in 162 adolescents wearing DAYTRANA 9 hours daily, the most common (≥ 10%) adverse reactions were decreased appetite and headache. A total of 9 subjects (5.5%) were withdrawn from the study due to adverse events and 3 additional subjects (1.9%) discontinued treatment as the result of an application site reaction. Other adverse reactions leading to discontinuation that occurred with a frequency of greater than 1% included affect lability and irritability (2 subjects each, 1.2%).

6.2 Postmarketing Experience

In addition, the following adverse reactions have been identified during the post-approval use of DAYTRANA. Because these reactions are reported voluntarily from a population of uncertain size, it is not possible to reliably estimate their frequency or establish a causal relationship to DAYTRANA exposure.

Cardiac Disorders: palpitations.

Eye Disorders: visual disturbances, blurred vision, increased intraocular pressure, mydriasis, and accommodation disorder.

General Disorders and Administration Site Disorders: fatigue, application site reactions such as bleeding, bruising, burn, burning, dermatitis, discharge, discoloration, discomfort, dryness, eczema, edema, erosion, erythema, excoriation, exfoliation, fissure, hyperpigmentation, hypopigmentation, induration, infection, inflammation, irritation, pain, papules, paresthesia, pruritus, rash, scab, swelling, ulcer, urticaria, vesicles, and warmth.

Immune System Disorders: hypersensitivity reactions including generalized erythematous and urticarial rashes, allergic contact dermatitis, angioedema, and anaphylaxis.

Investigations: blood pressure increased.

Nervous System Disorders: convulsion, dyskinesia, lethargy, somnolence, serotonin syndrome in combination with serotonergic drugs, and extrapyramidal disorder, motor, and verbal tics.

Psychiatric Disorders: depression, hallucination, nervousness, and libido changes.

Skin and Subcutaneous Tissue Disorders: alopecia.

Adverse Reactions with Oral Methylphenidate Products

Nervousness and insomnia are the most common adverse reactions reported with other methylphenidate products. In children, loss of appetite, abdominal pain, weight loss during prolonged therapy, insomnia, and tachycardia may occur more frequently; however, any of the other adverse reactions listed below may also occur.

Other reactions include:

Cardiac Disorders: angina, arrhythmia, and pulse increased or decreased.

Immune System Disorders: hypersensitivity reactions including skin rash, urticaria, fever, arthralgia, exfoliative dermatitis, erythema multiforme with histopathological findings of necrotizing vasculitis, and thrombocytopenic purpura.

Metabolism and Nutrition Disorders: anorexia and weight loss during prolonged therapy.

Nervous System Disorders: drowsiness, rare reports of Tourette's syndrome and toxic psychosis.

Very rare reports of neuroleptic malignant syndrome (NMS) have been received, and, in most of these, patients were concurrently receiving therapies associated with NMS. In a single report, a ten-year-old boy who had been taking methylphenidate for approximately 18 months experienced an NMS-like event within 45 minutes of ingesting his first dose of venlafaxine. It is uncertain whether this case represented a drug-drug interaction, a response to either drug alone, or some other cause.

Vascular Disorders: blood pressure increased or decreased and cerebral arteritis and/or occlusion.

Although a definite causal relationship has not been established, the following have been reported in patients taking methylphenidate:

Blood and Lymphatic System Disorders: leukopenia and/or anemia.

Hepatobiliary Disorders: abnormal liver function, ranging from transaminase elevation to severe hepatic injury.

Psychiatric Disorders: transient depressed mood.

Skin and Subcutaneous Tissue Disorders: scalp hair loss.

Musculoskeletal and Connective Tissue Disorders: rhabdomyolysis.

7 DRUG INTERACTIONS

7.1 Monoamine Oxidase Inhibitors (MAOI)

Concomitant use of MAOIs and CNS stimulants, including DAYTRANA, can cause hypertensive crisis. Potential outcomes include death, stroke, myocardial infarction, aortic dissection, ophthalmological complications, eclampsia, pulmonary edema, and renal failure [see Contraindications (4.2)]. Concomitant use of DAYTRANA with MAOIs or within 14 days after discontinuing MAOI treatment is contraindicated.

7.2 Antihypertensive Drugs

DAYTRANA may decrease the effectiveness of drugs used to treat hypertension. Monitor blood pressure and adjust the dosage of the antihypertensive drug as needed [see Warnings and Precautions (5.2)].

7.3 Coumarin Anticoagulants, Antidepressants, and Selective Serotonin Reuptake Inhibitors

Human pharmacologic studies have shown that methylphenidate may inhibit the metabolism of coumarin anticoagulants, anticonvulsants (e.g., phenobarbital, phenytoin, primidone), and some tricyclic drugs (e.g., imipramine, clomipramine, desipramine) and selective serotonin reuptake inhibitors. Downward dose adjustments of these drugs may be required when given concomitantly with methylphenidate. It may be necessary to adjust the dosage and monitor plasma drug concentrations (or, in the case of coumarin, coagulation times), when initiating or discontinuing methylphenidate.

7.4 Halogenated Anesthetics

Concomitant use of halogenated anesthetics and methylphenidate may increase the risk of sudden blood pressure and heart rate increase during surgery. Avoid use of DAYTRANA in patients being treated with anesthetics on the day of surgery.

7.5 Risperidone

Combined use of methylphenidate with risperidone when there is a change in dosage, whether an increase or decrease, of either or both medications, may increase the risk of extrapyramidal symptoms (EPS). Monitor for signs of EPS.

8 USE IN SPECIFIC POPULATIONS

8.1 Pregnancy

Pregnancy Exposure Registry

There is a pregnancy exposure registry that monitors pregnancy outcomes in women exposed to ADHD medications, including DAYTRANA, during pregnancy. Healthcare providers are encouraged to register patients by calling the National Pregnancy Registry for ADHD Medications at 1-866-961-2388 or visit https://womensmentalhealth.org/adhd-medications/.

Risk Summary

Published studies and post-marketing reports on methylphenidate use during pregnancy are insufficient to identify a drug-associated risk of major birth defects, miscarriage or adverse maternal or fetal outcomes. There are risks to the fetus associated with the use of CNS stimulants during pregnancy (see Clinical Considerations).

No effects on morphological development were observed in embryo-fetal development studies with oral administration of methylphenidate to pregnant rats and rabbits during organogenesis. However, spina bifida was observed in rabbits when given oral doses of 200 mg/kg/day. When methylphenidate was administered orally to rats throughout pregnancy and lactation, offspring growth and survival were decreased at maternally toxic doses (see Data).

The estimated background risk of major birth defects and miscarriage for the indicated population is unknown. All pregnancies have a background risk of birth defect, loss, or other adverse outcomes. In the U.S. general population, the estimated background risk of major birth defects and miscarriage in clinical recognized pregnancies is 2-4% and 15-20%, respectively.

Clinical Considerations

Fetal/Neonatal adverse reactions

CNS stimulants, such as DAYTRANA, can cause vasoconstriction and thereby decrease placental perfusion. No fetal and/or neonatal adverse reactions have been reported with the use of therapeutic doses of methylphenidate during pregnancy; however, premature delivery and low birth weight infants have been reported in amphetamine-dependent mothers.

Data

Animal Data

Animal reproduction toxicity studies with transdermal methylphenidate have not been performed. In embryo-fetal development studies conducted in rats and rabbits, methylphenidate was administered orally to pregnant animals during the period of organogenesis, at doses up to 100 and 200 mg/kg/day, respectively. No evidence of morphological development effects was found in either of the species; however, increased incidences of fetal skeletal variations were observed in rats at 60 mg/kg or greater and an increase in fetal visceral variations was seen in rabbits at the highest dose. In a previous study, methylphenidate was shown to have malformations (increased incidence of fetal spina bifida) in rabbits when given oral doses of 200 mg/kg/day. When methylphenidate was administered orally to rats throughout pregnancy and lactation at doses of up to 60 mg/kg/day, offspring growth and survival were decreased at maternally toxic doses.

In a study in which oral methylphenidate was given to rats throughout pregnancy and lactation at doses up to 60 mg/kg/day, offspring weights and survival were decreased at 40 mg/kg/day and above; these doses caused some maternal toxicity.

8.2 Lactation

Risk Summary

Limited published literature, based on breast milk sampling from five mothers, reports that methylphenidate is present in human milk, which resulted in infant doses of 0.16% to 0.7% of the maternal weight-adjusted dosage and a milk/plasma ratio ranging between 1.1 and 2.7. There are no reports of adverse effects on the breastfed infant and no effects on milk production. Long-term neurodevelopmental effects on infants from stimulant exposure are unknown. The developmental and health benefits of breastfeeding should be considered along with the mother’s clinical need for DAYTRANA and any potential adverse effects on the breastfed infant from DAYTRANA or from the underlying maternal condition.

Clinical Considerations

Monitor breastfeeding infants for adverse reactions, such as agitation, insomnia, anorexia, and reduced weight gain.

8.4 Pediatric Use

The safety and effectiveness of DAYTRANA have not been established in pediatric patients below the age of 6 years.

In studies evaluating extended-release methylphenidate products, patients 4 to <6 years of age had higher systemic methylphenidate exposures than those observed in older pediatric patients at the same dosage. Pediatric patients 4 to <6 years of age also had a higher incidence of adverse reactions, including weight loss.

The safety and effectiveness of DAYTRANA for the treatment of ADHD have been established in pediatric patients 6 to 17 years.

Long Term Suppression of Growth

Growth should be monitored during treatment with stimulants, including DAYTRANA. Children who are not growing or gaining weight as expected may need to have their treatment interrupted [see Warnings and Precautions (5.8)].

Juvenile Animal Toxicity Data

Rats treated with methylphenidate early in the postnatal period through sexual maturation demonstrated a decrease in spontaneous locomotor activity in adulthood. A deficit in acquisition of a specific learning task was observed in females only.

Studies with transdermal methylphenidate have not been performed in juvenile animals. In a study conducted in young rats, methylphenidate was administered orally at doses of up to 100 mg/kg/day for 9 weeks, starting early in the postnatal period (Postnatal Day 7) and continuing through sexual maturity (Postnatal Week 10). When these animals were tested as adults (Postnatal Weeks 13-14), decreased spontaneous locomotor activity was observed in males and females previously treated with 50 mg/kg/day or greater, and a deficit in the acquisition of a specific learning task was seen in females exposed to the highest dose. The no effect level for juvenile neurobehavioral development in rats was 5 mg/kg/day. The clinical significance of the long-term behavioral effects observed in rats is unknown.

8.5 Geriatric Use

DAYTRANA has not been studied in patients greater than 65 years of age.

9 DRUG ABUSE AND DEPENDENCE

9.1 Controlled Substance

DAYTRANA contains methylphenidate, a Schedule II controlled substance.

9.2 Abuse

DAYTRANA has a high potential for abuse and misuse which can lead to the development of a substance use disorder, including addiction [see Warnings and Precautions (5.1)]. DAYTRANA can be diverted for non-medical use into illicit channels or distribution.

Abuse is the intentional non-therapeutic use of a drug, even once, to achieve a desired psychological or physiological effect. Misuse is the intentional use, for therapeutic purposes, of a drug by an individual in a way other than prescribed by a health care provider or for whom it was not prescribed. Drug addiction is a cluster of behavioral, cognitive, and physiological phenomena that may include a strong desire to take the drug, difficulties in controlling drug use (e.g., continuing drug use despite harmful consequences, giving a higher priority to drug use than other activities and obligations), and possible tolerance or physical dependence.

Misuse and abuse of methylphenidate may cause increased heart rate, respiratory rate, or blood pressure; sweating; dilated pupils; hyperactivity; restlessness; insomnia; decreased appetite; loss of coordination; tremors; flushed skin; vomiting; and/or abdominal pain. Anxiety, psychosis, hostility, aggression, and suicidal or homicidal ideation have also been observed with CNS stimulants abuse and/or misuse. Misuse and abuse of CNS stimulants, including DAYTRANA, can result in overdose and death [see Overdosage (10)], and this risk is increased with higher doses or unapproved methods of administration, such as snorting or injection.

9.3 Dependence

Physical Dependence

DAYTRANA may produce physical dependence. Physical dependence is a state that develops as a result of physiological adaptation in response to repeated drug use, manifested by withdrawal signs and symptoms after abrupt discontinuation or a significant dose reduction of a drug.

Withdrawal signs and symptoms after abrupt discontinuation or dose reduction following prolonged use of CNS stimulants including DAYTRANA include dysphoric mood; depression; fatigue; vivid, unpleasant dreams; insomnia or hypersomnia; increased appetite; and psychomotor retardation or agitation.

Tolerance

DAYTRANA may produce tolerance. Tolerance is a physiological state characterized by a reduced response to a drug after repeated administration (i.e., a higher dose of a drug is required to produce the same effect that was once obtained at a lower dose).

10 OVERDOSAGE

Clinical Effects of Overdose

Overdose of CNS stimulants is characterized by the following sympathomimetic effects:

- Cardiovascular effects including tachyarrhythmias, and hypertension or hypotension. Vasospasm, myocardial infarction, or aortic dissection may precipitate sudden cardiac death. Takotsubo cardiomyopathy may develop.
- CNS effects including psychomotor agitation, confusion, and hallucinations. Serotonin syndrome, seizures, cerebral vascular accidents, and coma may occur.
- Life-threatening hyperthermia (temperatures greater than 104°F) and rhabdomyolysis may develop.

Overdose Management

Consider the possibility of multiple drug ingestion. Because methylphenidate has a large volume of distribution and is rapidly metabolized, dialysis is not useful. Remove all transdermal systems immediately and cleanse the area(s) to remove any remaining adhesive. The continuing absorption of methylphenidate from the skin, even after removal of the transdermal system, should be considered when treating patients with overdose.

Consider contacting the Poison Help line (1-800-222-1222) or a medical toxicologist for additional overdose management recommendations.

11 DESCRIPTION

DAYTRANA is an adhesive-based matrix transdermal system containing methylphenidate that is applied to intact skin. The chemical name for methylphenidate is α-phenyl-2-piperidineacetic acid methyl ester. It is a white to off-white powder and is soluble in alcohol, ethyl acetate, and ether. Methylphenidate is practically insoluble in water and petrol ether. Its molecular weight is 233.31. Its empirical formula is C14 H19 NO2. The structural formula of methylphenidate is:

Transdermal System Components

DAYTRANA contains methylphenidate in a multipolymeric adhesive. The methylphenidate is dispersed in acrylic adhesive that is dispersed in a silicone adhesive. The composition per unit area of all dosage strengths is identical, and the total dose delivered is dependent on the transdermal system size and wear time.

DAYTRANA consists of three layers, as seen in the figure below (cross-section of the transdermal system).

Proceeding from the outer surface toward the surface adhering to the skin, the layers are (1) a polyester/ethylene vinyl acetate laminate film backing, (2) a proprietary adhesive formulation incorporating Noven Pharmaceuticals, Inc.'s DOT Matrix™ transdermal technology consisting of an acrylic adhesive, a silicone adhesive, and methylphenidate, and (3) a fluoropolymer-coated polyester protective liner, which is attached to the adhesive surface and must be removed before the transdermal system can be used.

The active component of the transdermal system is methylphenidate. The remaining components are pharmacologically inactive.

12 CLINICAL PHARMACOLOGY

12.1 Mechanism of Action

Methylphenidate is a CNS stimulant. Its mode of therapeutic action in ADHD is not known.

12.2 Pharmacodynamics

Methylphenidate is a racemic mixture comprised of the d-and l-enantiomers. The d-enantiomer is more pharmacologically active than the l-enantiomer. Methylphenidate blocks the reuptake of norepinephrine and dopamine into the presynaptic neuron and increases the release of these monoamines into the extraneuronal space.

12.3 Pharmacokinetics

The pharmacokinetics of DAYTRANA when applied to the hip for 9 hours have been studied in ADHD patients 6 to 17 years old.

Absorption

The amount of methylphenidate absorbed systemically is a function of both wear time and transdermal system size. In patients with ADHD, peak plasma levels of methylphenidate are reached at about 10 hours after single application and 8 hours after repeat transdermal system applications (12.5cm^2 to 37.5cm^2) when worn up to 9 hours.

On single dosing of children or adolescents with DAYTRANA, there was a delay of, on average, 2 hours before d-methylphenidate was detectable in the circulation. On repeat dosing, low concentrations (1.2-3.0 ng/mL in children and 0.5-1.7ng/mL in adolescents, on average across the dose range) were observed earlier in the profile, due to carry-over effect. Following the application of DAYTRANA once daily with a 9-hour wear time, the mean pharmacokinetic parameters of d-methylphenidate in children and adolescents with ADHD after 4 weeks of therapy are summarized in Table 3.

Table 3
Mean Plasma d-Methylphenidate Pharmacokinetic Parameters After Repeated 9-Hour Applications of DAYTRANA or Oral ER-MPH for up to 28 days to Pediatric ADHD Patients (Aged 6 - 17 years)
Children
Parameter | DAYTRANA ^1 12.5cm ^2 (N=12) | DAYTRANA ^2 37.5cm ^2 (N=10) | Oral ER-MPH ^3 18mg | Oral ER-MPH ^3 54mg
C ssmax (ng/mL) | 15.7 ± 9.39 | 42.9 ± 22.4 | 8.37 ± 4.14 | 26.1 ± 11.2
C ssmin (ng/mL) | 1.04 ± 1.17 | 1.96 ± 1.73 | 0.708 ± 1.08 | 1.19 ± 1.54
AUC ss (ng·hr/mL) | 163 ± 101 | 447 ± 230 | 97.7 ± 67.0 | 317 ± 160
t lag (h) ^4 | 0 (0 - 2.0) | 0 (0 - 1.0) | 0 | 0
Adolescents
C ssmax (ng/mL) | 8.32 ± 4.60 | 16.5 ± 6.94 | 5.23 ± 1.72 | 18.0 ± 6.97
C ssmin (ng/mL) | 0.544 ± 0.383 | 1.02 ± 0.629 | 0.360 ± 0.478 | 1.50 ± 0.937
AUC ss (ng·hr/mL) | 85.7 ± 50.0 | 167 ± 66.0 | 59.7 ± 19.1 | 216 ± 80.8
t lag (h) ^4 | 0 (0 - 2.0) | 0 (0 - 2.0) | 0 | 0
^1 Dose maintained fixed for 28 days;
^2 Dose escalated at 7 day intervals from 12.5 cm^2 through 18.75 cm^2 and 25 cm^2 to 37.5 cm^2;
^3 Dose escalated at 7 day intervals from 18 mg through 27 mg and 36 mg to 54 mg;
^4 Median (minimum - maximum); t lag = Last Sampling Time Prior to Time of First Quantifiable Plasma Concentration

Following administration of DAYTRANA 12.5cm^2 to pediatric and adolescent ADHD patients daily for 7 days, there were 13% and 14% increases, respectively, in steady state area under the plasma concentration-time curve (AUC ss) relative to that anticipated on the basis of single dose pharmacokinetics (AUC0 -∞); after 28 days administration, these increments increased to 64% and 76%, respectively. C max increased by nearly 69% and 100% within 4 weeks of daily administration of the starting dose in children and adolescents, respectively.

The observed exposures with DAYTRANA could not be explained by drug accumulation predicted from observed single dose pharmacokinetics and there was no evidence that clearance or rate of elimination changed between single and repeat dosing. Neither were they explainable by differences in dosing patterns between treatments, age, race, or gender. This suggests that transdermal absorption of methylphenidate may increase with repeat dosing with DAYTRANA; on average, steady-state is likely to have been achieved by approximately 14 days of dosing.

In the single- and multiple dose study described above, exposure to l-methylphenidate was 46% of the exposure to d-methylphenidate in children and 40% in adolescents. l-methylphenidate is less pharmacologically active than d-methylphenidate [see Pharmacodynamics (12.2)] .

In a phase 2 PK/PD study in children aged 6-12 years, 2/3 of patients had 2-hour d-MPH concentrations < 5 ng/mL on chronic dosing, and at 3 hours 40% of patients had d-MPH concentrations < 5 ng/mL [see Clinical Studies (14)] .

When DAYTRANA is applied to inflamed skin both the rate and extent of absorption are increased as compared with intact skin. When applied to inflamed skin, lag time is no greater than 1 hour, T max is 4 hours, and both C max and AUC are approximately 3-fold higher.

When heat is applied to DAYTRANA after application, both the rate and the extent of absorption are significantly increased. Median T lag occurs 1 hour earlier, T max occurs 0.5 hours earlier, and median C max and AUC are 2-fold and 2.5-fold higher, respectively.

Application sites other than the hip can have different absorption characteristics and have not been adequately studied in safety or efficacy studies.

Dose Proportionality

Following a single 9-hour application of DAYTRANA doses of 10 mg / 9 hours to 30 mg / 9 hours transdermal systems to 34 children with ADHD, C max and AUC 0-t of d-methylphenidate were proportional to the transdermal system dose. Mean plasma concentration-time plots are shown in Figure 1. C max of l-methylphenidate was also proportional to the transdermal system dose. AUC 0-t of l-methylphenidate was only slightly greater than proportional to transdermal system dose.

Distribution

Upon removal of DAYTRANA, methylphenidate plasma concentrations in children with ADHD decline in a biexponential manner. This may be due to continued distribution of MPH from the skin after transdermal system removal.

Metabolism and Excretion

Methylphenidate is metabolized primarily by de-esterification to alpha-phenyl-piperidine acetic acid (ritalinic acid), which has little or no pharmacologic activity.

Transdermal administration of methylphenidate exhibits much less first pass effect than oral administration. Consequently, a much lower dose of DAYTRANA on a mg/kg basis compared to oral dosages may still produce higher exposures of d-MPH with transdermal administration compared to oral administration. In addition, very little, if any, l-methylphenidate is systemically available after oral administration due to first pass metabolism, whereas after transdermal administration of racemic methylphenidate exposure to l-methylphenidate is nearly as high as to d-methylphenidate.

The mean elimination t 1/2 from plasma of d-methylphenidate after removal of DAYTRANA in children aged 6 to 12 years and adolescents aged 13-17 years was approximately 4 to 5 hours. The t 1/2 of l-methylphenidate was shorter than for d-methylphenidate and ranged from 1.4 to 2.9 hours, on average.

The C max and AUC of d-methylphenidate were approximately 50% lower in adolescents, compared to children, following either a 1-day or 7-day administration of DAYTRANA (10mg/9hr). Multiple-dose administration of DAYTRANA did not result in significant accumulation of methylphenidate; following 7 days of DAYTRANA administration (10mg/9hr) in children and adolescents, the accumulation index of methylphenidate was 1.1, based on the mean steady state area under the plasma concentration-time curve (AUC ss) relative to that anticipated on the basis of single dose pharmacokinetics (AUC 0-∞).

Food Effects

The pharmacokinetics or the pharmacodynamic food effect performance after application of DAYTRANA has not been studied, but because of the transdermal route of administration, no food effect is expected.

Special Populations

Gender

The pharmacokinetics of methylphenidate after single and repeated doses of DAYTRANA were similar between boys and girls with ADHD, after allowance for differences in body weight.

Race

The influence of race on the pharmacokinetics of methylphenidate after administration of DAYTRANA has not been defined.

Age

The pharmacokinetics of methylphenidate after administration of DAYTRANA have not been studied in children less than 6 years of age.

Renal Impairment

There is no experience with the use of DAYTRANA in patients with renal insufficiency.

Hepatic Impairment

There is no experience with the use of DAYTRANA in patients with hepatic insufficiency.

13 NONCLINICAL TOXICOLOGY

13.1 Carcinogenesis/Mutagenesis and Impairment of Fertility

Carcinogenesis

Carcinogenicity studies of transdermal methylphenidate have not been performed. In a lifetime carcinogenicity study of oral methylphenidate carried out in B6C3F1 mice, methylphenidate caused an increase in hepatocellular adenomas and, in males only, an increase in hepatoblastomas, at a daily dose of approximately 60 mg/kg/day. Hepatoblastoma is a relatively rare rodent malignant tumor type. There was no increase in total malignant hepatic tumors. The mouse strain used is sensitive to the development of hepatic tumors and the significance of these results to humans is unknown.

Orally administered methylphenidate did not cause any increases in tumors in a lifetime carcinogenicity study carried out in F344 rats; the highest dose used was approximately 45 mg/kg/day.

In a 24-week oral carcinogenicity study in the transgenic mouse strain p53+/-, which is sensitive to genotoxic carcinogens, there was no evidence of carcinogenicity. In this study, male and female mice were fed diets containing the same concentration of methylphenidate as in the lifetime carcinogenicity study; the high-dose groups were exposed to 60 to 74 mg/kg/day of methylphenidate.

Mutagenesis

Methylphenidate was not mutagenic in the in vitro Ames reverse mutation assay or in the in vitro mouse lymphoma cell forward mutation assay. Sister chromatid exchanges and chromosome aberrations were increased, indicative of a weak clastogenic response, in an in vitro assay in cultured Chinese hamster ovary cells. Methylphenidate was negative in vivo in males and females in the mouse bone marrow micronucleus assay.

Impairment of Fertility

Methylphenidate did not impair fertility in male or female mice that were fed diets containing the drug in an 18-week continuous breeding study. The study was conducted at doses up to 160 mg/kg/day.

14 CLINICAL STUDIES

DAYTRANA was demonstrated to be effective in the treatment of ADHD in two (2) randomized double-blind, placebo-controlled studies in children aged 6 to 12 years and one (1) randomized, double-blind, placebo-controlled study in adolescents aged 13 to 17 years who met Diagnostic and Statistical Manual (DSM-IV-TR®) criteria for ADHD. DAYTRANA wear time was 9 hours in all three (3) studies.

In Study 1, conducted in a classroom setting, symptoms of ADHD were evaluated by school teachers and observers using the Deportment Subscale from the Swanson, Kotkin, Agler, M-Flynn, and Pelham (SKAMP) rating scale which assesses behavior symptoms in the classroom setting. DAYTRANA was applied for 9 hours before removal. There was a 5-week open-label DAYTRANA dose optimization phase using dosages of 10, 15, 20, and 30 mg / 9 hours, followed by a 2-week randomized, double-blind, placebo-controlled crossover treatment phase using the optimal transdermal system dose for each patient or placebo. The mean differences between DAYTRANA and placebo in change from baseline in SKAMP Deportment Scores were statistically significant in favor of DAYTRANA beginning at 2 hours and remained statistically significant at all subsequent measured time points through 12 hours after application of the DAYTRANA.

In Study 2, conducted in the outpatient setting, DAYTRANA or placebo was blindly administered in a flexible-dose design using doses of 10, 15, 20, and 30 mg / 9 hours to achieve an optimal regimen over 5 weeks, followed by a 2-week maintenance period using the optimal transdermal system dose for each patient. Symptoms of ADHD were evaluated by the ADHD-Rating Scale (RS)-IV. DAYTRANA was statistically significantly superior to placebo as measured by the mean change from baseline for the ADHD-RS-IV total score. Although this study was not designed specifically to evaluate dose response, in general there did not appear to be any additional effectiveness accomplished by increasing the transdermal system dose from 20 mg / 9 hours to 30 mg / 9 hours.

In Study 3, conducted in the outpatient setting, DAYTRANA or placebo was blindly administered in a flexible-dose design using doses of 10, 15, 20, and 30 mg / 9 hours during a 5-week dose-optimization phase, followed by a 2-week maintenance period using the optimal transdermal system dose for each patient. Symptoms of ADHD were evaluated using the ADHD-Rating Scale (RS)-IV. DAYTRANA was statistically significantly superior to placebo as measured by the mean change from baseline in the ADHD-RS-IV total score.

16 HOW SUPPLIED/STORAGE AND HANDLING

DAYTRANA is supplied in a sealed tray containing 30 individually pouched transdermal systems. See the chart below for information regarding available strengths.

Nominal Dose Delivered (mg) Over 9 Hours | Dosage Rate* (mg/hr) | Transdermal System Size (cm ^2) | Methylphenidate Content per Transdermal System** (mg) | Transdermal Systems Per Carton | NDC Number
10 | 1.1 | 12.5 | 27.5 | 30 | 68968-5552-3
15 | 1.6 | 18.75 | 41.3 | 30 | 68968-5553-3
20 | 2.2 | 25 | 55 | 30 | 68968-5554-3
30 | 3.3 | 37.5 | 82.5 | 30 | 68968-5555-3
*Nominal in vivo delivery rate per hour in children and adolescents when applied to the hip, based on a 9-hour wear period.
**Methylphenidate content in each transdermal system.

Store at 25° C (77° F); excursions permitted to 15-30° C (59-86° F) [see USP Controlled Room Temperature]. Do not store transdermal systems unpouched. Do not store transdermal systems in refrigerators or freezers.

Once the sealed tray is opened, use contents within 2 months. Apply the transdermal system immediately upon removal from the individual protective pouch. For transdermal use only.

See the Patient Counseling Information (17) for specific disposal instructions for unused or expired DAYTRANA.

17 PATIENT COUNSELING INFORMATION

Advise patients to read the FDA-approved patient labeling (Medication Guide and Instructions for Use).

Abuse, Misuse, and Addiction

Educate patients and their families about the risks of abuse, misuse, and addiction of DAYTRANA, which can lead to overdose and death, and proper disposal of any unused drug [see Warnings and Precautions (5.1), Drug Abuse and Dependence (9.2), Overdosage (10)]. Advise patients to store DAYTRANA in a safe place, preferably locked, and instruct patients to not give DAYTRANA to anyone else.

Special Disposal Instructions

Advise patients that there are special disposal instructions for unused or expired DAYTRANA [see Warnings and Precautions (5.1)]. Instruct patients to find a take back location to dispose of unused or expired DAYTRANA. If a take back program is unavailable, instruct them to:

1. Remove DAYTRANA from its pouch, separate it from its liner, fold it in half with the adhesive sides touching each other, and immediately flush it down the toilet, and
2. Place the pouch and liner in a container, close the container, and throw out the container in the trash (advise patients not to flush the pouch and liner down the toilet).

Risks to Patients with Serious Cardiac Disease

Advise patients that there are potential risks to patients with serious cardiac disease, including sudden death, with DAYTRANA use. Instruct patients to contact a healthcare provider immediately if they develop symptoms, such as exertional chest pain, unexplained syncope, or other symptoms suggestive of cardiac disease [see Warnings and Precautions (5.2)].

Priapism

Advise patients, caregivers, and family members of the possibility of painful or prolonged penile erections (priapism). Instruct the patient to seek immediate medical attention in the event of priapism [see Warnings and Precautions (5.6)].

Circulation problems in fingers and toes [Peripheral vasculopathy, including Raynaud’s phenomenon] [see Warnings and Precautions (5.7)]

- Instruct patients beginning treatment with DAYTRANA about the risk of peripheral vasculopathy, including Raynaud’s Phenomenon, and in associated signs and symptoms: fingers or toes may feel numb, cool, painful, and/or may change color from pale, to blue, to red.
- Instruct patients to report to their physician any new numbness, pain, skin color change, or sensitivity to temperature in fingers or toes.
- Instruct patients to call their physician immediately with any signs of unexplained wounds appearing on fingers or toes while using DAYTRANA.
- Further clinical evaluation (e.g., rheumatology referral) may be appropriate for certain patients.

Long-Term Suppression of Growth in Pediatric Patients

Advise patients that DAYTRANA may cause slowing of growth including weight loss [see Warnings and (5.8)].

Chemical Leukoderma

Advise patients of the possibility of a persistent loss of skin pigmentation at, around and distant from the application site. Advise patients to immediately inform their healthcare provider if changes in skin pigmentation occur [see Warnings and Precautions (5.9)].

Increased Intraocular Pressure (IOP) and Glaucoma

Advise patients that IOP and glaucoma may occur during treatment with DAYTRANA [see Warnings and Precautions (5.14)].

Motor and Verbal Tics, and Worsening of Tourette’s Syndrome

Advise patients that motor and verbal tics and worsening of Tourette’s Syndrome may occur during treatment with DAYTRANA. Instruct patients to notify their healthcare provider if emergence of new tics or worsening of tics or Tourette’s syndrome occurs [see Warnings and Precautions (5.15)].

Important Preparation and Administration Instructions [see Dosage and Administration (2.3)]

- Parents and patients should be informed to apply DAYTRANA to a clean, dry site on the hip, which is not oily, damaged, or irritated. The site of application must be alternated daily. DAYTRANA should not be applied to the waistline, or where tight clothing may rub it.
- If patients or caregivers experience difficulty separating the transdermal system from the release liner or observe tearing and/or other damage to the transdermal system during removal from the liner, the transdermal system should be discarded according to the directions provided in this label, and a new transdermal system should be applied [see Dosage and Administration (2.3)]. Patients or caregivers should inspect the release liner to ensure that no adhesive containing medication has transferred to the liner. If adhesive transfer has occurred, the transdermal system should be discarded.
- DAYTRANA should be applied 2 hours before the desired effect. DAYTRANA should be removed approximately 9 hours after it is applied, although the effects from the transdermal system will last for several more hours. DAYTRANA may be removed earlier than 9 hours if a shorter duration of effect is desired or late day side effects appear.
- The parent or caregiver should be encouraged to use the administration chart included with each carton of DAYTRANA to monitor application and removal time, and method of disposal. The Medication Guide included at the end of this insert also includes a timetable to calculate when to remove DAYTRANA, based on the 9 hour application time.
- Patients or caregivers should avoid touching the adhesive side of the transdermal system during application, in order to avoid absorption of methylphenidate. If they do touch the adhesive side of the transdermal system, they should immediately wash their hands after application.
- In the event that a DAYTRANA does not fully adhere to the skin upon application, or is partially or fully detached during wear time, the transdermal system should be discarded according to the directions provided in this label, and a new transdermal system should be applied [see Dosage and Administration (2.3)]. If a transdermal system is replaced, the total recommended wear time for that day should remain 9 hours, regardless of the number of transdermal systems used.
- DAYTRANA should not be applied or re-applied with dressings, tape, or other common adhesives.
- Exposure to water during bathing, swimming, or showering can affect DAYTRANA adherence.
- Do not cut transdermal systems. Only intact transdermal systems should be applied.
- If there is an unacceptable duration of appetite loss or insomnia in the evening, taking the transdermal system off earlier may be attempted before decreasing the transdermal system dose.
- Skin redness or itching is common with DAYTRANA and small bumps on the skin may also occur in some patients. If any swelling or blistering occurs the DAYTRANA should not be worn and the patient should be seen by the prescriber. Patients or caregivers should not apply hydrocortisone or other solutions, creams, ointments, or emollients immediately prior to DAYTRANA application, since the effect on transdermal system adhesion and methylphenidate absorption has not been established. The potential adverse effects of topical corticosteroid use during treatment with DAYTRANA are unknown.

Recommended Storage Instructions

Transdermal systems should be stored at 25 degrees Celsius (77 degrees Fahrenheit) with excursions permitted that do not exceed 15 to 30 degrees Celsius (59 to 86 degrees Fahrenheit) [see How Supplied/Storage and Handling (16)]. Patients or caregivers should be advised not to store DAYTRANA in the refrigerator or freezer.

Pregnancy Registry

Advise patients that there is a pregnancy exposure registry that monitors pregnancy outcomes in women exposed to ADHD medications, including DAYTRANA, during pregnancy [see Use in Specific Populations (8.1)].

Manufactured for: Noven Therapeutics, LLC, Miami, FL 33186.

By: Noven Pharmaceuticals, Inc., Miami, FL 33186.

For more information, call 1-800-455-8070 or visit www.daytrana.com.

DOT Matrix™ is a trademark of Noven Pharmaceuticals, Inc.
DAYTRANA® is a registered trademark of Noven Therapeutics, LLC.

102086-23

MEDICATION GUIDE

DAYTRANA® (day-TRON-ah)
(methylphenidate transdermal system) CII

Important: DAYTRANA is for use on the skin only.

What is the most important information I should know about DAYTRANA?

DAYTRANA may cause serious side effects, including:

- Abuse, misuse, and addiction. DAYTRANA has a high chance for abuse and misuse and may lead to substance use problems, including addiction. Misuse and abuse of DAYTRANA, other methylphenidate containing medicines, and amphetamine containing medicines, can lead to overdose and death. The risk of overdose and death is increased with higher doses of DAYTRANA or when it is used in ways that are not approved, such as snorting or injection.
  - Your healthcare provider should check your child's risk for abuse, misuse, and addiction before starting treatment with DAYTRANA and will monitor your child during treatment.
  - DAYTRANA may lead to physical dependence after prolonged use, even if taken as directed by your healthcare provider.
  - Do not give DAYTRANA to anyone else. See "What is DAYTRANA?" for more information.
  - Keep DAYTRANA in a safe place and properly dispose of any unused medicine. See "How should I store DAYTRANA?" for more information.
  - Tell your healthcare provider if your child has ever abused or been dependent on alcohol, prescription medicines, or street drugs.
- Risks for people with serious heart disease. Sudden death has happened in people who have heart defects or other serious heart disease.
  Your child's healthcare provider should check your child carefully for blood pressure and heart problems before starting treatment with and while you are using DAYTRANA. Tell your child's healthcare provider if your child has any heart problems, heart disease or heart defects.
  Remove the DAYTRANA transdermal system (patch) and call your child's healthcare provider or go to the nearest emergency room right away if your child has any signs of heart problems such as chest pain, shortness of breath, or fainting during treatment with DAYTRANA.
- Increased blood pressure and heart rate.
  Your child's healthcare provider should check your child's blood pressure and heart rate regularly during treatment with DAYTRANA.
- Mental (psychiatric) problems, including:
  - new or worse behavior or thought problems
  - new or worse bipolar illness
  - new psychotic symptoms (such as hearing voices, or seeing or believing things that are not real) or manic symptoms
  Tell your child's healthcare provider about any mental problems your child has or about a family history of suicide, bipolar illness, or depression.
  Call your child's healthcare provider right away if your child has any new or worsening mental symptoms or problems during treatment with DAYTRANA, especially hearing voices, seeing, or believing things that are not real, or new manic symptoms.

What is DAYTRANA?

DAYTRANA is a central nervous system (CNS) stimulant prescription medication used for the treatment of Attention Deficit Hyperactivity Disorder (ADHD) in children 6 to 17 years of age. DAYTRANA may help increase attention and decrease impulsiveness and hyperactivity in children with ADHD.

DAYTRANA is not recommended for use in children under 6 years of age with ADHD.

DAYTRANA is a federally controlled substance (CII) because it contains methylphenidate that can be a target for people who abuse prescription medicines or street drugs. Keep DAYTRANA in a safe place to protect it from theft. Never give your DAYTRANA to anyone else because it may cause death or harm them. Selling or giving away DAYTRANA may harm others and is against the law.

Do not use DAYTRANA if your child:

- is allergic to methylphenidate or any of the ingredients in DAYTRANA. See the end of this Medication Guide for a complete list of ingredients in DAYTRANA.
- is taking, or has stopped taking withing the past 14 days, a medicine used to treat depression called a monoamine oxidase inhibitor (MAOI)

Before using DAYTRANA, tell your child's healthcare provider about all of your child's medical conditions, including if your child:

- has heart problems, heart disease, heart defects, or high blood pressure
- has mental problems including psychosis, mania, bipolar illness, or depression, or has a family history of suicide bipolar illness, or depression
- has seizures or have had an abnormal brain wave test (EEG)
- has circulation problems in fingers or toes
- has skin problems such as eczema or psoriasis, or have skin reactions to soaps, lotions, make-up, or adhesives (glues)
- has a history of vitiligo or a family history of vitiligo
- has eye problems, including increased pressure in your eye, glaucoma, or problems with your close-up vision (farsightedness)
- has or had repeated movements or sounds (tics) or Tourettes syndrome, or have a family history of tics or Tourettes syndrome
- is pregnant or plans to become pregnant. It is not known if DAYTRANA will harm the unborn baby. Tell your child's healthcare provider if your child becomes pregnant during treatment with DAYTRANA.
  - There is a pregnancy registry for females who are exposed to DAYTRANA during pregnancy. The purpose of the registry is to collect information about the health of women exposed to DAYTRANA and their baby. If your child becomes pregnant during treatment with DAYTRANA, talk to your child's healthcare provider about registering with the National Pregnancy Registry of Psychostimulants at 1-866-961-2388 or visit online at https://womensmentalhealth.org/adhd-medications/.
- is breast feeding or plan to breast feed. DAYTRANA passes into breast milk. Talk to your child's healthcare provider about the best way to feed the baby during treatment with DAYTRANA.
- a history of vitiligo and/or a family history of vitiligo

Tell your child's healthcare provider about all of the medicines your child takes, including prescription and over-the-counter medicines, vitamins, and herbal supplements.

DAYTRANA and some medicines may interact with each other and cause serious side effects. Sometimes the doses of other medicines will need to be changed during treatment with DAYTRANA. Your child's healthcare provider will decide if DAYTRANA can be taken with other medicines.

Especially tell your child's healthcare provider if your child takes:

- blood pressure medicines (anti-hypertensive)

Know the medicines that your child takes. Keep a list of your child's medicines with you to show your child's healthcare provider and pharmacist when your child gets a new medicine. Do not start any new medicine while using DAYTRANA without first talking to your child's healthcare provider.

How should DAYTRANA be used?

- See the detailed “Instructions for Use” at the end of this Medication Guide for information about the right way to apply, remove, and dispose of DAYTRANA.
- Use DAYTRANA exactly as prescribed by your child's healthcare provider.
- Your child's healthcare provider may change the dose if needed.
- Apply DAYTRANA to the hip area 2 hours before an effect is needed and remove DAYTRANA within 9 hours after it is applied. Do not wear DAYTRANA longer than 9 hours a day.
- If DAYTRANA falls off, a new patch may be applied to a different area of the same hip.
- If you forget to apply DAYTRANA at your usual scheduled time each day, you may apply the patch later in the day. The patch should be removed at the usual time of day to lower the chance of side effects later in the day.
- If your child has loss of appetite or trouble sleeping in the evening, ask your child's healthcare provider if your child can take the patch off earlier in the day.
- Contact with water while bathing, swimming, or showering can make the patch not stick well.
- Do not use bandages, tape, or other household adhesives (glue) to hold the patch onto the skin.

If your child uses too much DAYTRANA transdermal systems call your healthcare provider or Poison Help line at 1-800-222-1222 or go to the nearest hospital emergency room right away.

What should your child avoid while using DAYTRANA?

- After applying the DAYTRANA patch, avoid exposing the application site to direct external heat sources, such as hair dryers, heating pads, electric blankets, heated water beds or other heat sources. Exposure to heat can cause too much medicine to pass into the body and cause serious side effects.

What are the possible side effects of DAYTRANA?

DAYTRANA may cause serious side effects, including:

- See "What is the most important information I should know about DAYTRANA?"
- Seizures. Your child's healthcare provider may stop treatment with DAYTRANA if your child has a seizure.
- Painful and prolonged erections (priapism). Priapism that may require surgery has happened in people who take products that contain methylphenidate. If your child develops priapism, get medical help right away.
- Circulation problems in fingers and toes (peripheral vasculopathy, including Raynauds phenomenon). Signs and symptoms may include:
  - fingers or toes may feel numb, cool, or painful
  - fingers and toes may change color from pale, to blue, to red
  Tell your child's healthcare provider if your child has any numbness, pain, skin color change, or sensitivity to temperature in the fingers or toes.
  Call your healthcare provider right away if your child has any signs of unexplained wounds appearing on fingers or toes during treatment with DAYTRANA.
- Slowing of growth (height and weight) in children. Your child should have their height and weight checked often during treatment with DAYTRANA. Your healthcare provider may stop your child’s DAYTRANA treatment if they are not growing or gaining weight as expected.
- Eyes problems (increased pressure in the eye and glaucoma). Call your healthcare provider right away if you or your child develop changes in your vision or eye pain, swelling, or redness.
- New or worsening tics or worsening Tourette's syndrome. Tell your healthcare provider if you or your child get any new or worsening tics or worsening Tourettes syndrome during treatment with DAYTRANA.
- Loss of skin color. DAYTRANA may cause a persistent loss of skin-color where the patch is applied or around the patch application site. Loss of skin-color, in some cases, has been reported at locations on the skin far from any application site. The loss of skin-color may be permanent even after removing the patch or DAYTRANA is stopped. Call your healthcare provider right away if your child has changes in skin-color. DAYTRANA treatment may be stopped if your child has changes in skin color.
- Allergic skin rash (contact sensitization). Stop using DAYTRANA and tell your child's healthcare provider right away if your child develops swelling or blisters at or around the application site. Your child may have a skin allergy to DAYTRANA. People who have skin allergies to DAYTRANA may develop an allergy to all medicines that contain methylphenidate, even methylphenidate medicines taken by mouth.

The most common side effects of DAYTRANA in children 6 to 12 years old include:

- decreased appetite
- trouble sleeping
- nausea

- vomiting
- weight loss
- tics

- changes in mood
- trouble eating

The most common side effects of DAYTRANA in children 13 to 17 years old include:

- decreased appetite
- nausea
- trouble sleeping

- weight loss
- dizziness

- stomach pain
- trouble eating

DAYTRANA may also cause skin problems where it is applied (redness, small bumps, itching)

Your child's doctor may do certain blood tests while your child uses DAYTRANA.

These are not all the possible side effects of DAYTRANA.

Call your doctor for medical advice about side effects. You may report side effects to FDA at 1-800-FDA-1088.

How should I store DAYTRANA?

- Store DAYTRANA at room temperature between 68° F to 77° F (20° C to 25° C).
- Store DAYTRANA in a safe place, like a locked cabinet.
- Do not store DAYTRANA in the refrigerator or freezer.
- Keep DAYTRANA in their unopened pouches until you are ready to use them.
- Use or throw away the patches within 2 months after you open the sealed tray.
- Dispose of remaining, unused, or expired DAYTRANA by a medicine take-back program at a U.S. Drug Enforcement Administration (DEA) authorized collection site. If no take-back program or DEA authorized collector is available, each unused patch should be removed from its individual pouch, separated from the protective liner, folded in half so that the sticky sides stick together, and flushed down the toilet. Put the pouch and liner in a container with a lid, close the container and throw away the container in the household trash. Do not flush the pouch and liner down the toilet. Visit www.fda.gov/drugdisposal for additional information on disposal of unused medicines.

Keep DAYTRANA and all medicines out of the reach of children.

General information about the safe and effective use of DAYTRANA.

Medicines are sometimes prescribed for purposes other than those listed in a Medication Guide. Do not use DAYTRANA for a condition for which it was not prescribed. Do not give DAYTRANA to other people, even if they have the same symptoms. It may harm them and it is against the law.

You can ask your pharmacist or healthcare provider for information about DAYTRANA that is written for healthcare professionals.

What are the ingredients in DAYTRANA?
Active ingredient: methylphenidate
Inactive ingredients: acrylic adhesive, silicone adhesive

Manufactured by: Noven Pharmaceuticals, Inc., Miami, FL 33186
DAYTRANA® is a trademark of Noven Therapeutics, LLC.

For more information, go to www.daytrana.com, or call 1-800-455-8070.

This Medication Guide has been approved by the U.S. Food and Drug Administration.

Revised 09/2025

INSTRUCTIONS FOR USE
DAYTRANA® (day-TRON-ah)
(methylphenidate transdermal system) CII

1. DAYTRANA Dosing Chart

Each carton of DAYTRANA contains a DAYTRANA Dosing Chart to help you keep track of your DAYTRANA transdermal system (patch) including:

- when you apply patch to the skin on your hip each morning
- when you remove the patch
- how and where you threw DAYTRANA away

To use the DAYTRANA Dosing Chart, follow these instructions:

- Each day, when a new patch is applied to your hip, write down the date and time that you applied the patch.
- Use the DAYTRANA schedule below so you can decide when to remove the patch. For example, if the patch is applied to the skin at 6:00 a.m., remove the patch at 3:00 p.m. on the same day. After you remove and throw away the patch, write down the time you removed the patch and how and where you threw it away.
- If the patch you placed on your child is missing, ask your child:
  - when the patch came off
  - how the patch came off
  - where the patch is

DAYTRANA Schedule for 9 Hour Dosing

If you put the patch on at: | On the same day, remove the patch at:
5:00 a.m. | 2:00 p.m.
6:00 a.m. | 3:00 p.m.
7:00 a.m. | 4:00 p.m.
8:00 a.m. | 5:00 p.m.
9:00 a.m. | 6:00 p.m.
10:00 a.m. | 7:00 p.m.
11:00 a.m. | 8:00 p.m.
12:00 p.m. | 9:00 p.m.

2. Where to apply DAYTRANA

- Apply patch to your hip area. Do not put the patch near your waist. Clothing and movement may make your patch rub off (See Figure A).
- Use your other hip when you apply a new patch the next morning. Make sure there is no redness, small bumps or itching at the site where the patch is going to be applied.

Figure A

3. Before you apply DAYTRANA

Make sure your skin:

- Is clean (freshly washed), dry, and cool
- Does not have any powder, oil, or lotion
- Does not have any cuts and irritation (rashes, inflammation, redness, or other skin problems).

4. How to apply DAYTRANA

- Open the sealed tray and throw away the small packet (drying agent).
- Each patch is sealed in its own protective pouch.
- Carefully cut the protective pouch open with scissors, being careful not to cut the patch. Do not use patches that have been cut or damaged in any way (See Figure B).

Figure B

- Remove the patch from the protective pouch.
- Look at the patch to make sure it is not damaged. The patch should separate easily from the protective liner. Throw away the patch if the protective liner is hard to remove.

DAYTRANA has 3 layers. The 3 layers are pictured below. The pictures show both sides of the patch:

Figure C Figure D

Layers:

- Protective liner: The protective liner is the layer that you remove before you put the patch on (See Figure C).
- Adhesive with medicine: The adhesive with medicine is the layer that sticks to your skin (See Figure C).
- Outside backing: The outside backing is the layer that you see after you put the patch on your skin. The word "Daytrana" is printed on this layer (See Figure D).

- Apply the patch right away after you remove the patch from protective pouch.
- Hold the patch with the hard protective liner facing you. The word DAYTRANA will appear backwards.
- Gently bend the patch along the faint line and slowly peel half the liner, which covers the sticky surface of the patch (See Figure E).

Figure E

- Avoid touching the sticky side of the patch with your fingers.
- If you accidentally touch the sticky side of the patch, apply the patch, then wash your hands right away so that the medicine does not go into the skin on your hands.
- Using the other half of the protective liner as a handle, apply the sticky side of the patch to the selected area of the child's hip (See Figure F).

Figure F

- Press the sticky side of the patch firmly into place and smooth it down.
- While you are still holding the sticky side down, gently fold back the other half of the patch.
- Hold an edge of the remaining protective liner and slowly peel it off (See Figure G).

Figure G

- After the protective liner is removed, there should not be any adhesive (glue) sticking to the liner.

Figure H

- Press the entire patch firmly into place with the palm of your hand over the patch for about 30 seconds (See Figure H).
- Make sure that the patch firmly sticks to your skin.
- Gently rub the edges of the patch with your fingers to make sure the patch sticks to your skin.
- Wash your hands after you apply your patch.
- Write the time you applied your patch on the dosing chart on the carton. Use the dosing schedule so you know what time you should remove your patch.

5. How to remove and throw away DAYTRANA

- When you remove the patch, peel it off slowly. If the patch is too sticky on your skin and you need something to help you remove it:
  - Gently apply an oil-based product (petroleum jelly, olive oil, or mineral oil) to the patch edges. Gently spread the oil underneath the patch edges.
  - Apply an oil-based product or lotion to your skin if any adhesive (glue) remains after you remove your patch. This will gently loosen and remove any adhesive that is left over.
  - If you still cannot easily remove the patch, ask your doctor or pharmacist about what to do for this problem.
- Fold the used patch in half and press it together firmly so that the sticky side sticks to itself. Flush the used patch down the toilet.
- Do not flush the protective pouches or the protective liners down the toilet. These items should be thrown away in a container with a lid.
- Wash your hands after you handle the patch.
- After you remove the patch and throw the patch away, write down the time on the dosing chart.
- Safely throw away any unused patches that are left over from the prescription as soon as they are no longer needed.
  To safely throw away the patches:
  - Remove the leftover patches from their protective pouches and remove the protective liners.
  - Either fold the patches in half with the sticky sides together, and flush the patches down the toilet, or
  - Dispose of remaining, unused, or expired DAYTRANA by a medicine take-back program at a U.S. Drug Enforcement Administration (DEA) authorized collection site. If no take-back program or DEA authorized collector is available, each unused patch should be removed from its individual pouch, separated from the protective liner, folded in half so that the sticky sides stick together, and flushed down the toilet. Put the pouch and liner in a container with a lid, close the container and throw away the container in the household trash. Do not flush the pouch and liner down the toilet. Visit www.fda.gov/drugdisposal for additional information on disposal of unused medicines.

Manufactured for: Noven Therapeutics, LLC, Miami, FL 33186.

By: Noven Pharmaceuticals, Inc., Miami, FL 33186.
This Instructions for Use has been approved by the U.S. Food and Drug Administration.

Revised: 11/2024

102086-23

PACKAGE LABEL

PRINCIPAL DISPLAY PANEL - NDC 68968-5552-3 - 10 mg 30 Count Carton

NDC 68968-5552-3

Daytrana®

(methylphenidate transdermal system)

Delivers 10 mg over 9 hours

(1.1 mg/hr)

Patch should be worn for approximately 9 hours

Contains: 30 Patches

CII

Rx only

Noven Therapeutics, LLC

Once the tray is opened, use contents within 2 months.

Manufactured for Noven Therapeutics, LLC, Miami, FL 33186

By Noven Pharmaceuticals, Inc.

©2007, 2010 Noven Pharmaceuticals, Inc.

1-877-567-7857

Pharmacists: Enclosed Medication Guide to be dispensed to each patient.

302188-8 Rev. 9/2016

Each patch contains 27.5 mg of methylphenidate.

Active ingredient release is limited; please see recommended dosing in patient instructions.

Inactive components: acrylic adhesive, coextruded backing film, polyester release liner and silicone adhesive.

For transdermal use only (applied only to skin).

Keep all patches within provided containers and dispense one patch daily. Apply immediately upon removal from pouch.

Do not store unpouched. Do not store patches in refrigerators or freezers.

Store at 25°C (77°F); excursions permitted to 15-30°C (59-86°F) [see USP controlled Room Temperature]

Important: Keep out of the reach of children.

It is important that this product be disposed of properly. See patient instructions for disposal information.

Dosage and Administration: See package insert.

Date of Patch Application; MM/DD/YYYY | Time Applied | Time Removed | Application Side | Disposal Method | Date of Patch Application; MM/DD/YYYY | Time Applied | Time Removed | Application Side | Disposal Method
 | _AM _PM | _AM _PM | _Right _Left | _Fold & flush; _ Fold & trash |  | _AM _PM | _AM _PM | _Right _Left | _Fold & flush; _ Fold & trash
 | _AM _PM | _AM _PM | _Right _Left | _Fold & flush; _ Fold & trash |  | _AM _PM | _AM _PM | _Right _Left | _Fold & flush; _ Fold & trash
 | _AM _PM | _AM _PM | _Right _Left | _Fold & flush; _ Fold & trash |  | _AM _PM | _AM _PM | _Right _Left | _Fold & flush; _ Fold & trash
 | _AM _PM | _AM _PM | _Right _Left | _Fold & flush; _ Fold & trash |  | _AM _PM | _AM _PM | _Right _Left | _Fold & flush; _ Fold & trash
 | _AM _PM | _AM _PM | _Right _Left | _Fold & flush; _ Fold & trash |  | _AM _PM | _AM _PM | _Right _Left | _Fold & flush; _ Fold & trash
 | _AM _PM | _AM _PM | _Right _Left | _Fold & flush; _ Fold & trash |  | _AM _PM | _AM _PM | _Right _Left | _Fold & flush; _ Fold & trash
 | _AM _PM | _AM _PM | _Right _Left | _Fold & flush; _ Fold & trash |  | _AM _PM | _AM _PM | _Right _Left | _Fold & flush; _ Fold & trash
 | _AM _PM | _AM _PM | _Right _Left | _Fold & flush; _ Fold & trash |  | _AM _PM | _AM _PM | _Right _Left | _Fold & flush; _ Fold & trash
 | _AM _PM | _AM _PM | _Right _Left | _Fold & flush; _ Fold & trash |  | _AM _PM | _AM _PM | _Right _Left | _Fold & flush; _ Fold & trash
 | _AM _PM | _AM _PM | _Right _Left | _Fold & flush; _ Fold & trash |  | _AM _PM | _AM _PM | _Right _Left | _Fold & flush; _ Fold & trash
 | _AM _PM | _AM _PM | _Right _Left | _Fold & flush; _ Fold & trash |  | _AM _PM | _AM _PM | _Right _Left | _Fold & flush; _ Fold & trash
 | _AM _PM | _AM _PM | _Right _Left | _Fold & flush; _ Fold & trash |  | _AM _PM | _AM _PM | _Right _Left | _Fold & flush; _ Fold & trash
 | _AM _PM | _AM _PM | _Right _Left | _Fold & flush; _ Fold & trash |  | _AM _PM | _AM _PM | _Right _Left | _Fold & flush; _ Fold & trash
 | _AM _PM | _AM _PM | _Right _Left | _Fold & flush; _ Fold & trash |  | _AM _PM | _AM _PM | _Right _Left | _Fold & flush; _ Fold & trash
 | _AM _PM | _AM _PM | _Right _Left | _Fold & flush; _ Fold & trash |  | _AM _PM | _AM _PM | _Right _Left | _Fold & flush; _ Fold & trash

PACKAGE LABEL

PRINCIPAL DISPLAY PANEL - NDC 68968-5553-3 - 15 mg 30 Count Carton

NDC 68968-5553-3

Daytrana®

(methylphenidate transdermal system)

Delivers 15 mg over 9 hours

(1.6 mg/hr)

Patch should be worn for approximately 9 hours

Contains: 30 Patches

CII

Rx only

Noven Therapeutics, LLC

Once the tray is opened, use contents within 2 months.

Manufactured for Noven Therapeutics, LLC, Miami, FL 33186

By Noven Pharmaceuticals, Inc.

©2007, 2010 Noven Pharmaceuticals, Inc.

1-877-567-7857

Pharmacists: Enclosed Medication Guide to be dispensed to each patient.

302189-8 Rev. 9/2016

Each patch contains 41.3 mg of methylphenidate.

Active ingredient release is limited; please see recommended dosing in patient instructions.

Inactive components: acrylic adhesive, coextruded backing film, polyester release liner and silicone adhesive.

For transdermal use only (applied only to skin).

Keep all patches within provided containers and dispense one patch daily. Apply immediately upon removal from pouch.

Do not store unpouched. Do not store patches in refrigerators or freezers.

Store at 25°C (77°F); excursions permitted to 15-30°C (59-86°F) [see USP controlled Room Temperature]

Important: Keep out of the reach of children.

It is important that this product be disposed of properly. See patient instructions for disposal information.

Dosage and Administration: See package insert.

Date of Patch Application; MM/DD/YYYY | Time Applied | Time Removed | Application Side | Disposal Method | Date of Patch Application; MM/DD/YYYY | Time Applied | Time Removed | Application Side | Disposal Method
 | _AM _PM | _AM _PM | _Right _Left | _Fold & flush; _ Fold & trash |  | _AM _PM | _AM _PM | _Right _Left | _Fold & flush; _ Fold & trash
 | _AM _PM | _AM _PM | _Right _Left | _Fold & flush; _ Fold & trash |  | _AM _PM | _AM _PM | _Right _Left | _Fold & flush; _ Fold & trash
 | _AM _PM | _AM _PM | _Right _Left | _Fold & flush; _ Fold & trash |  | _AM _PM | _AM _PM | _Right _Left | _Fold & flush; _ Fold & trash
 | _AM _PM | _AM _PM | _Right _Left | _Fold & flush; _ Fold & trash |  | _AM _PM | _AM _PM | _Right _Left | _Fold & flush; _ Fold & trash
 | _AM _PM | _AM _PM | _Right _Left | _Fold & flush; _ Fold & trash |  | _AM _PM | _AM _PM | _Right _Left | _Fold & flush; _ Fold & trash
 | _AM _PM | _AM _PM | _Right _Left | _Fold & flush; _ Fold & trash |  | _AM _PM | _AM _PM | _Right _Left | _Fold & flush; _ Fold & trash
 | _AM _PM | _AM _PM | _Right _Left | _Fold & flush; _ Fold & trash |  | _AM _PM | _AM _PM | _Right _Left | _Fold & flush; _ Fold & trash
 | _AM _PM | _AM _PM | _Right _Left | _Fold & flush; _ Fold & trash |  | _AM _PM | _AM _PM | _Right _Left | _Fold & flush; _ Fold & trash
 | _AM _PM | _AM _PM | _Right _Left | _Fold & flush; _ Fold & trash |  | _AM _PM | _AM _PM | _Right _Left | _Fold & flush; _ Fold & trash
 | _AM _PM | _AM _PM | _Right _Left | _Fold & flush; _ Fold & trash |  | _AM _PM | _AM _PM | _Right _Left | _Fold & flush; _ Fold & trash
 | _AM _PM | _AM _PM | _Right _Left | _Fold & flush; _ Fold & trash |  | _AM _PM | _AM _PM | _Right _Left | _Fold & flush; _ Fold & trash
 | _AM _PM | _AM _PM | _Right _Left | _Fold & flush; _ Fold & trash |  | _AM _PM | _AM _PM | _Right _Left | _Fold & flush; _ Fold & trash
 | _AM _PM | _AM _PM | _Right _Left | _Fold & flush; _ Fold & trash |  | _AM _PM | _AM _PM | _Right _Left | _Fold & flush; _ Fold & trash
 | _AM _PM | _AM _PM | _Right _Left | _Fold & flush; _ Fold & trash |  | _AM _PM | _AM _PM | _Right _Left | _Fold & flush; _ Fold & trash
 | _AM _PM | _AM _PM | _Right _Left | _Fold & flush; _ Fold & trash |  | _AM _PM | _AM _PM | _Right _Left | _Fold & flush; _ Fold & trash

PACKAGE LABEL

PRINCIPAL DISPLAY PANEL - NDC 68968-5554-3 - 20 mg 30 Count Carton

NDC 68968-5554-3

Daytrana®

(methylphenidate transdermal system)

Delivers 20 mg over 9 hours

(2.2 mg/hr)

Patch should be worn for approximately 9 hours

Contains: 30 Patches

CII

Rx only

Noven Therapeutics, LLC

Once the tray is opened, use contents within 2 months.

Manufactured for Noven Therapeutics, LLC, Miami, FL 33186

By Noven Pharmaceuticals, Inc.

©2007, 2010 Noven Pharmaceuticals, Inc.

1-877-567-7857

Pharmacists: Enclosed Medication Guide to be dispensed to each patient.

302190-8 Rev. 9/2016

Each patch contains 55 mg of methylphenidate.

Active ingredient release is limited; please see recommended dosing in patient instructions.

Inactive components: acrylic adhesive, coextruded backing film, polyester release liner and silicone adhesive.

For transdermal use only (applied only to skin).

Keep all patches within provided containers and dispense one patch daily. Apply immediately upon removal from pouch.

Do not store unpouched. Do not store patches in refrigerators or freezers.

Store at 25°C (77°F); excursions permitted to 15-30°C (59-86°F) [see USP controlled Room Temperature]

Important: Keep out of the reach of children.

It is important that this product be disposed of properly. See patient instructions for disposal information.

Dosage and Administration: See package insert.

Date of Patch Application; MM/DD/YYYY | Time Applied | Time Removed | Application Side | Disposal Method | Date of Patch Application; MM/DD/YYYY | Time Applied | Time Removed | Application Side | Disposal Method
 | _AM _PM | _AM _PM | _Right _Left | _Fold & flush; _ Fold & trash |  | _AM _PM | _AM _PM | _Right _Left | _Fold & flush; _ Fold & trash
 | _AM _PM | _AM _PM | _Right _Left | _Fold & flush; _ Fold & trash |  | _AM _PM | _AM _PM | _Right _Left | _Fold & flush; _ Fold & trash
 | _AM _PM | _AM _PM | _Right _Left | _Fold & flush; _ Fold & trash |  | _AM _PM | _AM _PM | _Right _Left | _Fold & flush; _ Fold & trash
 | _AM _PM | _AM _PM | _Right _Left | _Fold & flush; _ Fold & trash |  | _AM _PM | _AM _PM | _Right _Left | _Fold & flush; _ Fold & trash
 | _AM _PM | _AM _PM | _Right _Left | _Fold & flush; _ Fold & trash |  | _AM _PM | _AM _PM | _Right _Left | _Fold & flush; _ Fold & trash
 | _AM _PM | _AM _PM | _Right _Left | _Fold & flush; _ Fold & trash |  | _AM _PM | _AM _PM | _Right _Left | _Fold & flush; _ Fold & trash
 | _AM _PM | _AM _PM | _Right _Left | _Fold & flush; _ Fold & trash |  | _AM _PM | _AM _PM | _Right _Left | _Fold & flush; _ Fold & trash
 | _AM _PM | _AM _PM | _Right _Left | _Fold & flush; _ Fold & trash |  | _AM _PM | _AM _PM | _Right _Left | _Fold & flush; _ Fold & trash
 | _AM _PM | _AM _PM | _Right _Left | _Fold & flush; _ Fold & trash |  | _AM _PM | _AM _PM | _Right _Left | _Fold & flush; _ Fold & trash
 | _AM _PM | _AM _PM | _Right _Left | _Fold & flush; _ Fold & trash |  | _AM _PM | _AM _PM | _Right _Left | _Fold & flush; _ Fold & trash
 | _AM _PM | _AM _PM | _Right _Left | _Fold & flush; _ Fold & trash |  | _AM _PM | _AM _PM | _Right _Left | _Fold & flush; _ Fold & trash
 | _AM _PM | _AM _PM | _Right _Left | _Fold & flush; _ Fold & trash |  | _AM _PM | _AM _PM | _Right _Left | _Fold & flush; _ Fold & trash
 | _AM _PM | _AM _PM | _Right _Left | _Fold & flush; _ Fold & trash |  | _AM _PM | _AM _PM | _Right _Left | _Fold & flush; _ Fold & trash
 | _AM _PM | _AM _PM | _Right _Left | _Fold & flush; _ Fold & trash |  | _AM _PM | _AM _PM | _Right _Left | _Fold & flush; _ Fold & trash
 | _AM _PM | _AM _PM | _Right _Left | _Fold & flush; _ Fold & trash |  | _AM _PM | _AM _PM | _Right _Left | _Fold & flush; _ Fold & trash

PACKAGE LABEL

PRINCIPAL DISPLAY PANEL - NDC 68968-5555-3 - 30 mg 30 Count Carton

NDC 68968-5555-3

Daytrana®

(methylphenidate transdermal system)

Delivers 30 mg over 9 hours

(3.3 mg/hr)

Patch should be worn for approximately 9 hours

Contains: 30 Patches

CII

Rx only

Noven Therapeutics, LLC

Once the tray is opened, use contents within 2 months.

Manufactured for Noven Therapeutics, LLC, Miami, FL 33186

By Noven Pharmaceuticals, Inc.

©2007, 2010 Noven Pharmaceuticals, Inc.

1-877-567-7857

Pharmacists: Enclosed Medication Guide to be dispensed to each patient.

302191-8 Rev. 9/2016

Each patch contains 82.5 mg of methylphenidate.

Active ingredient release is limited; please see recommended dosing in patient instructions.

Inactive components: acrylic adhesive, coextruded backing film, polyester release liner and silicone adhesive.

For transdermal use only (applied only to skin).

Keep all patches within provided containers and dispense one patch daily. Apply immediately upon removal from pouch.

Do not store unpouched. Do not store patches in refrigerators or freezers.

Store at 25°C (77°F); excursions permitted to 15-30°C (59-86°F) [see USP controlled Room Temperature]

Important: Keep out of the reach of children.

It is important that this product be disposed of properly. See patient instructions for disposal information.

Dosage and Administration: See package insert.

Date of Patch Application; MM/DD/YYYY | Time Applied | Time Removed | Application Side | Disposal Method | Date of Patch Application; MM/DD/YYYY | Time Applied | Time Removed | Application Side | Disposal Method
 | _AM _PM | _AM _PM | _Right _Left | _Fold & flush; _ Fold & trash |  | _AM _PM | _AM _PM | _Right _Left | _Fold & flush; _ Fold & trash
 | _AM _PM | _AM _PM | _Right _Left | _Fold & flush; _ Fold & trash |  | _AM _PM | _AM _PM | _Right _Left | _Fold & flush; _ Fold & trash
 | _AM _PM | _AM _PM | _Right _Left | _Fold & flush; _ Fold & trash |  | _AM _PM | _AM _PM | _Right _Left | _Fold & flush; _ Fold & trash
 | _AM _PM | _AM _PM | _Right _Left | _Fold & flush; _ Fold & trash |  | _AM _PM | _AM _PM | _Right _Left | _Fold & flush; _ Fold & trash
 | _AM _PM | _AM _PM | _Right _Left | _Fold & flush; _ Fold & trash |  | _AM _PM | _AM _PM | _Right _Left | _Fold & flush; _ Fold & trash
 | _AM _PM | _AM _PM | _Right _Left | _Fold & flush; _ Fold & trash |  | _AM _PM | _AM _PM | _Right _Left | _Fold & flush; _ Fold & trash
 | _AM _PM | _AM _PM | _Right _Left | _Fold & flush; _ Fold & trash |  | _AM _PM | _AM _PM | _Right _Left | _Fold & flush; _ Fold & trash
 | _AM _PM | _AM _PM | _Right _Left | _Fold & flush; _ Fold & trash |  | _AM _PM | _AM _PM | _Right _Left | _Fold & flush; _ Fold & trash
 | _AM _PM | _AM _PM | _Right _Left | _Fold & flush; _ Fold & trash |  | _AM _PM | _AM _PM | _Right _Left | _Fold & flush; _ Fold & trash
 | _AM _PM | _AM _PM | _Right _Left | _Fold & flush; _ Fold & trash |  | _AM _PM | _AM _PM | _Right _Left | _Fold & flush; _ Fold & trash
 | _AM _PM | _AM _PM | _Right _Left | _Fold & flush; _ Fold & trash |  | _AM _PM | _AM _PM | _Right _Left | _Fold & flush; _ Fold & trash
 | _AM _PM | _AM _PM | _Right _Left | _Fold & flush; _ Fold & trash |  | _AM _PM | _AM _PM | _Right _Left | _Fold & flush; _ Fold & trash
 | _AM _PM | _AM _PM | _Right _Left | _Fold & flush; _ Fold & trash |  | _AM _PM | _AM _PM | _Right _Left | _Fold & flush; _ Fold & trash
 | _AM _PM | _AM _PM | _Right _Left | _Fold & flush; _ Fold & trash |  | _AM _PM | _AM _PM | _Right _Left | _Fold & flush; _ Fold & trash
 | _AM _PM | _AM _PM | _Right _Left | _Fold & flush; _ Fold & trash |  | _AM _PM | _AM _PM | _Right _Left | _Fold & flush; _ Fold & trash